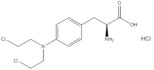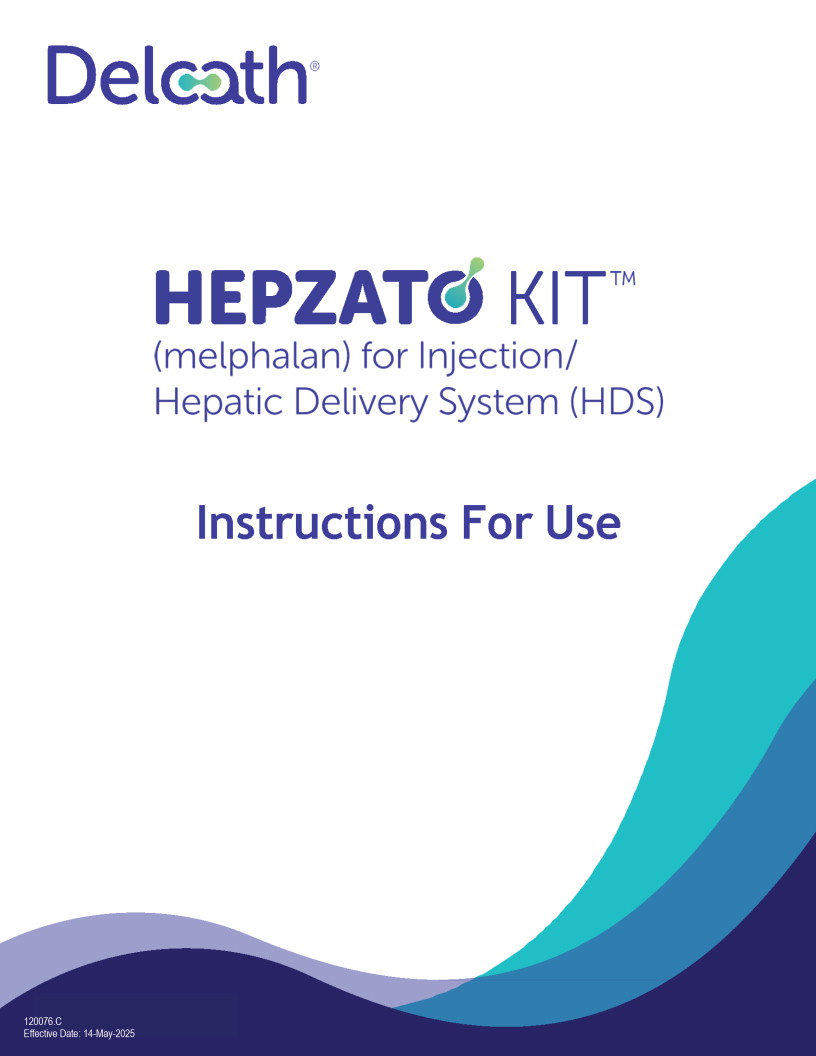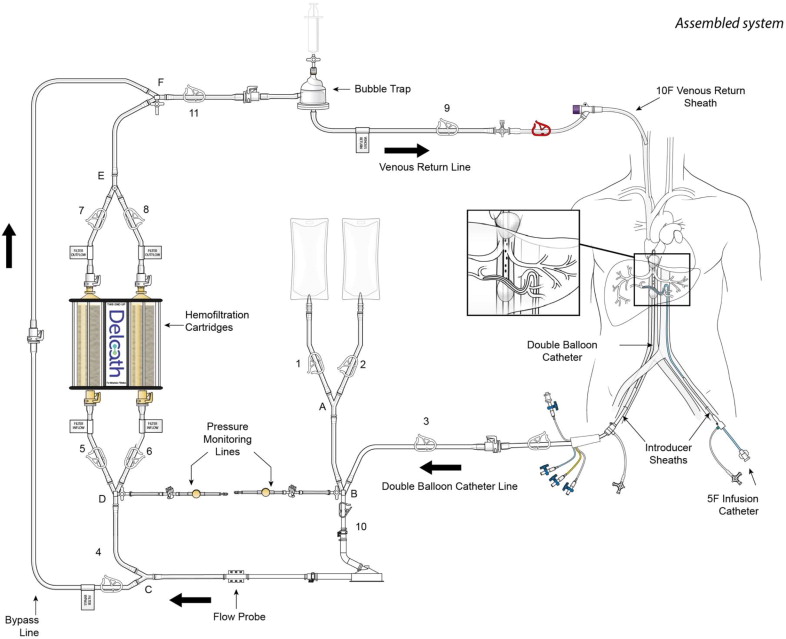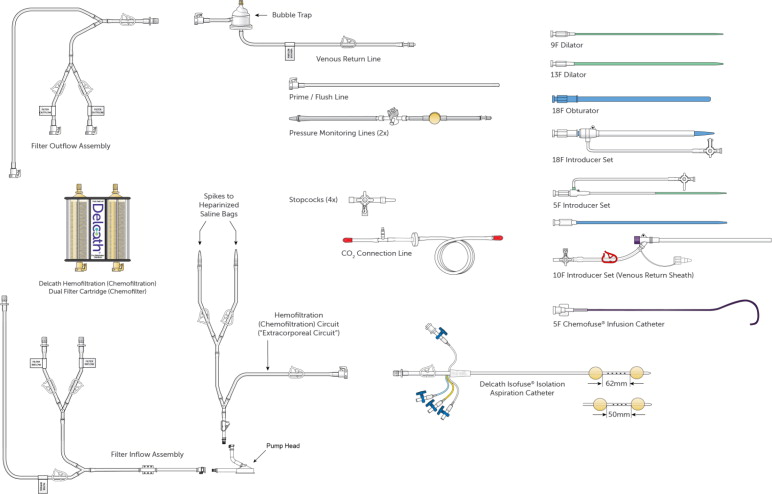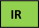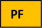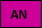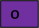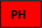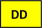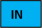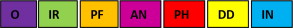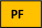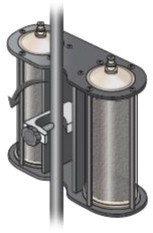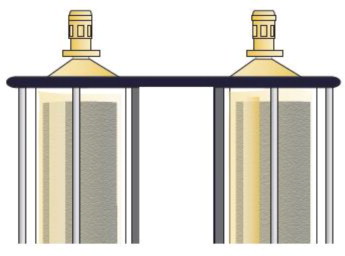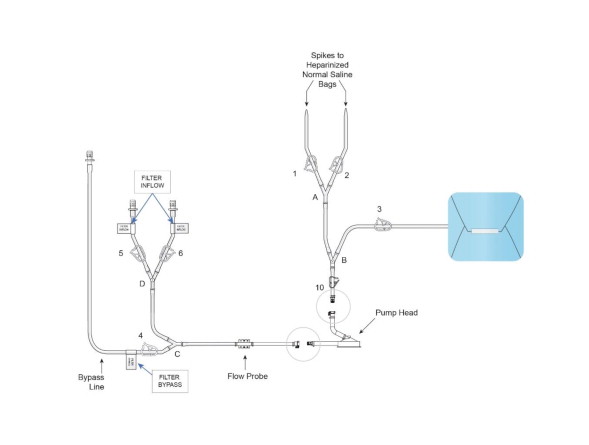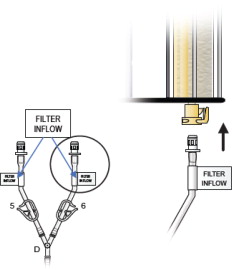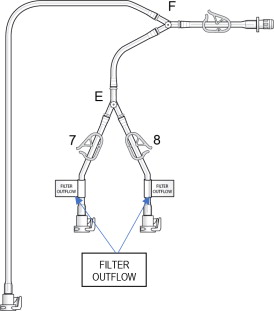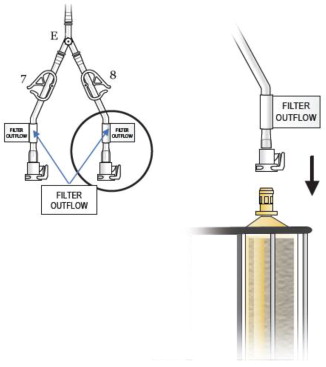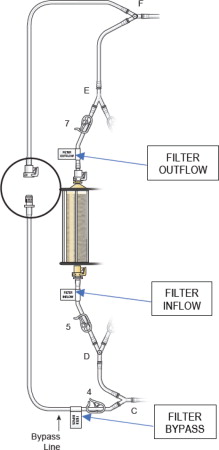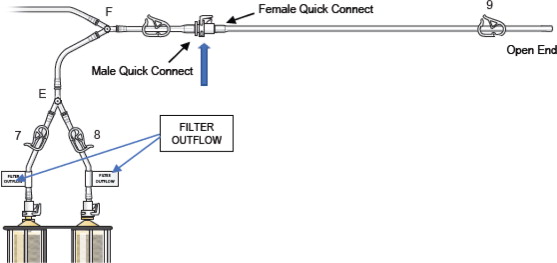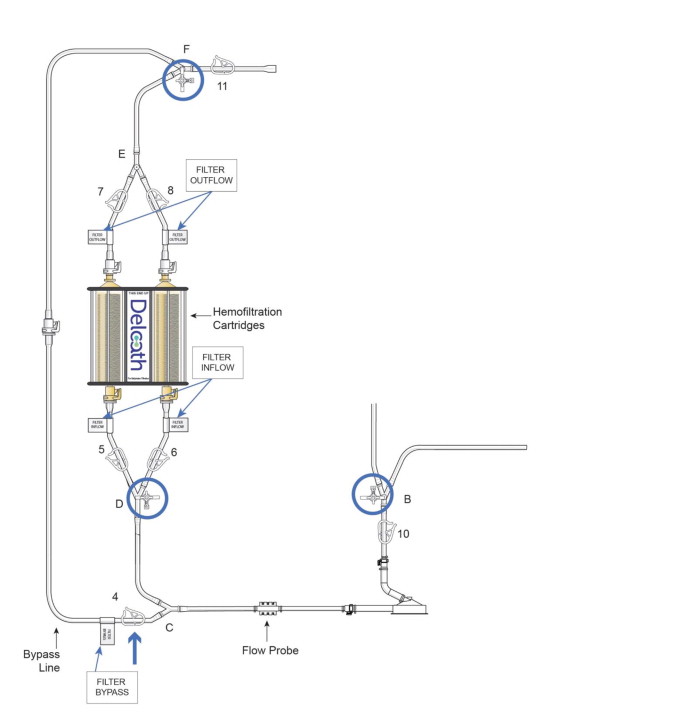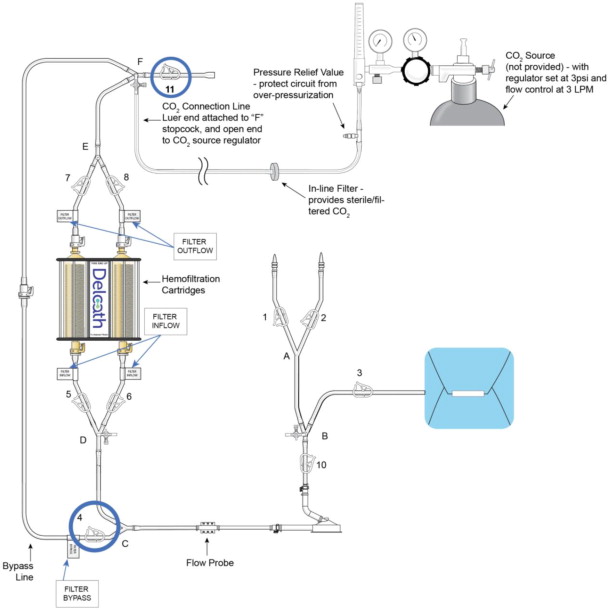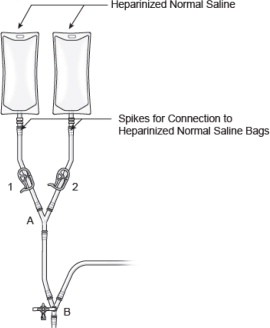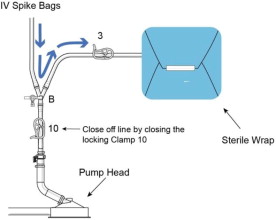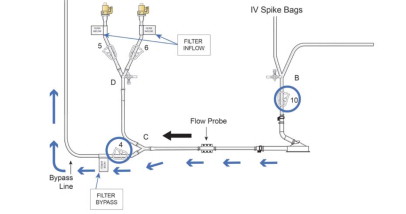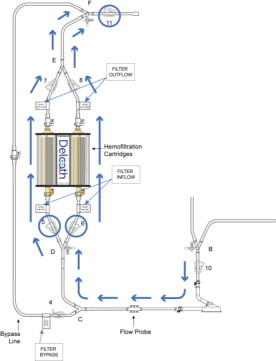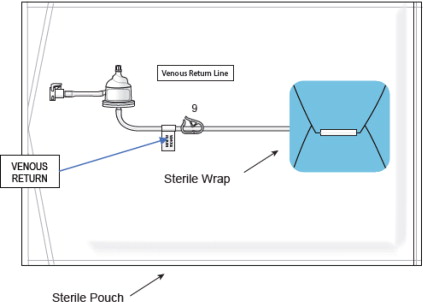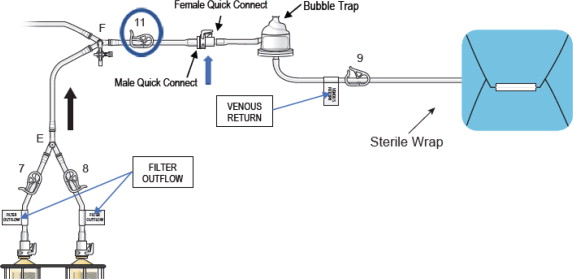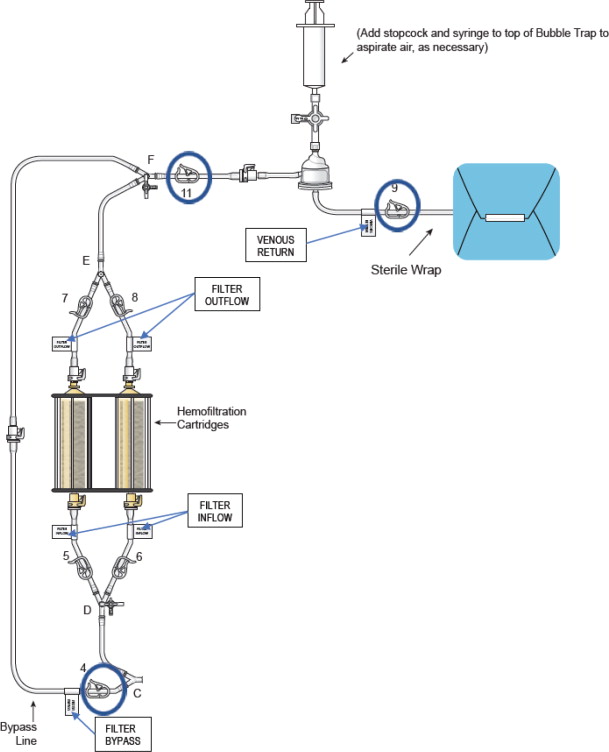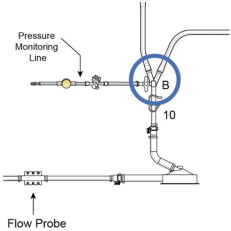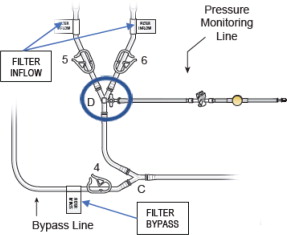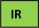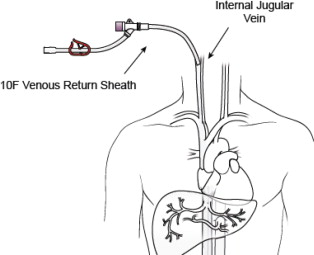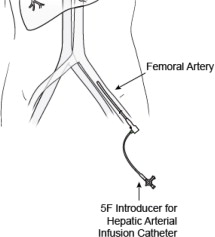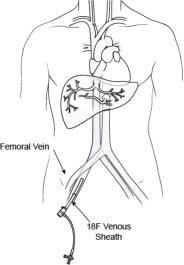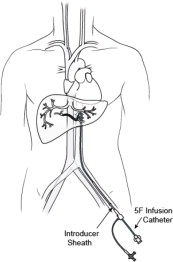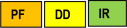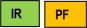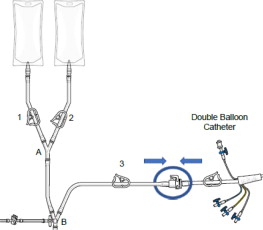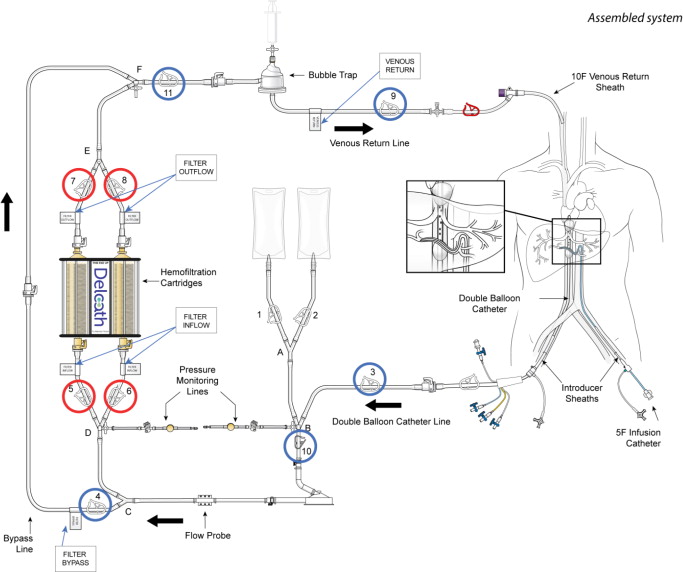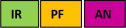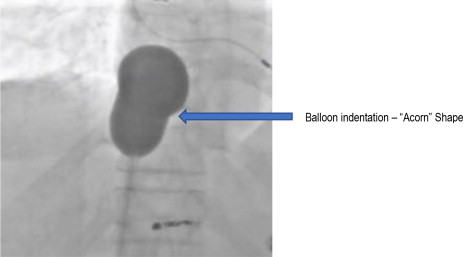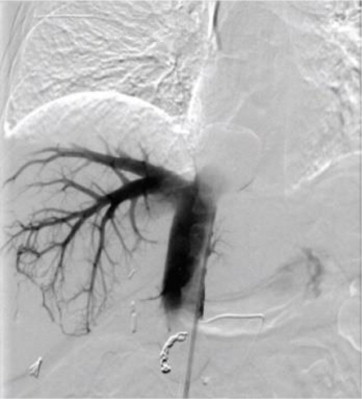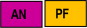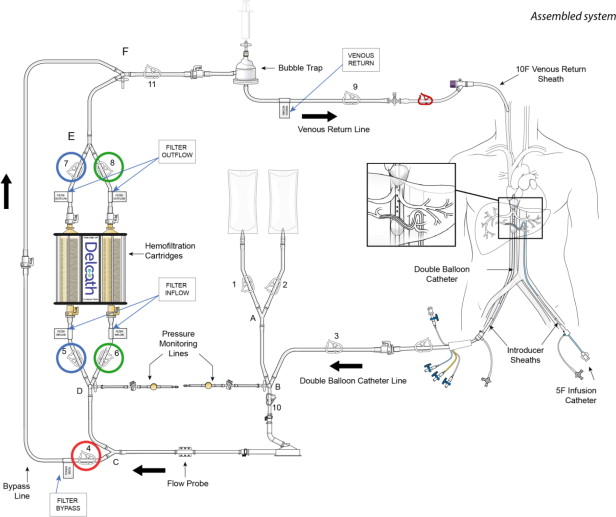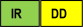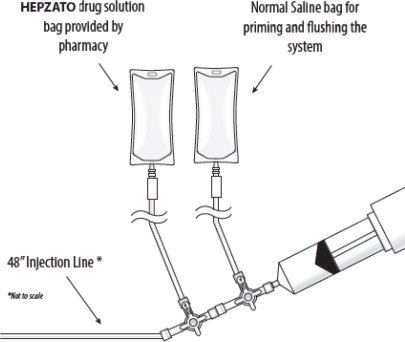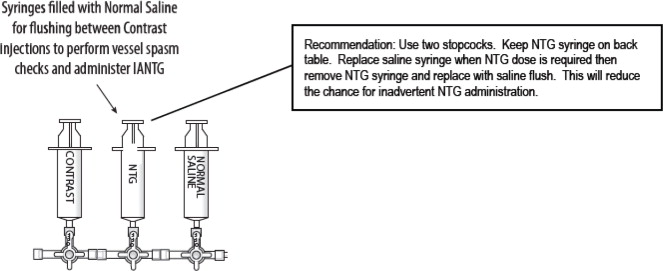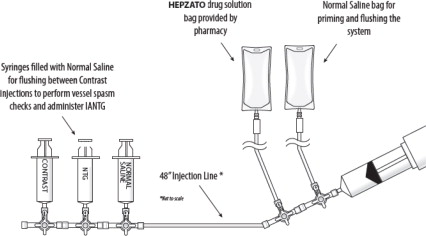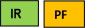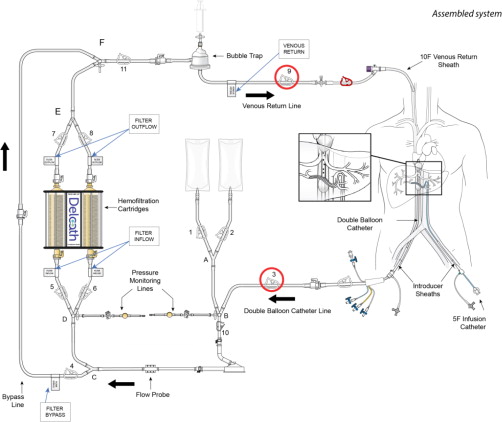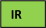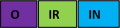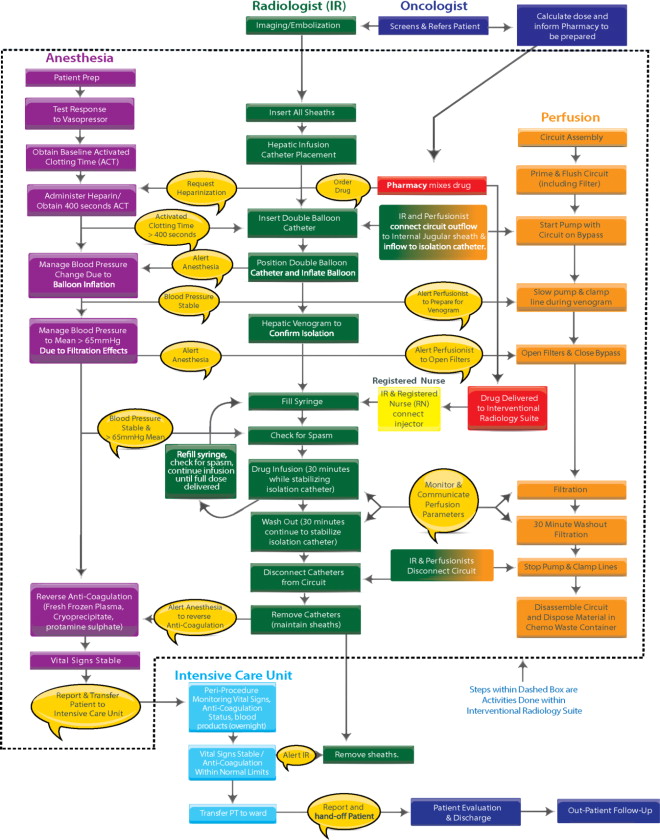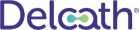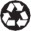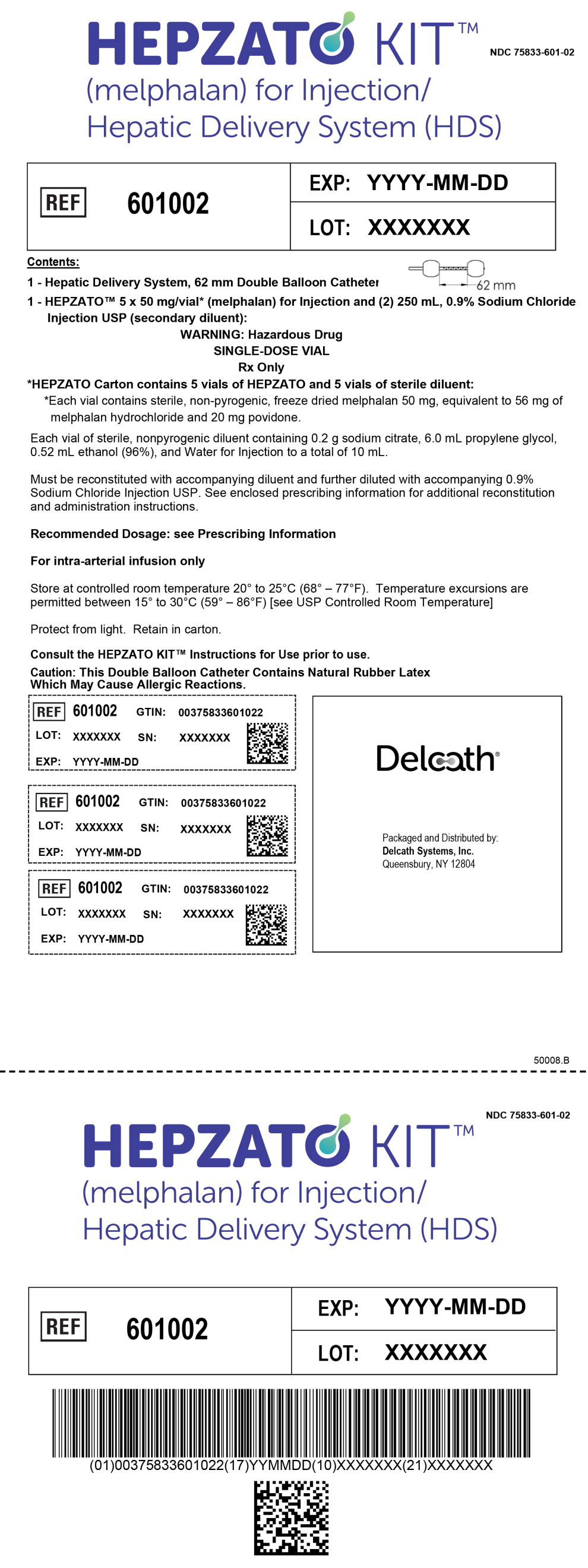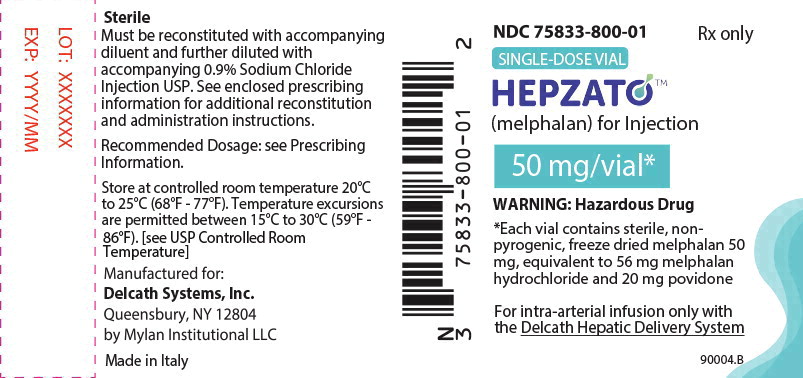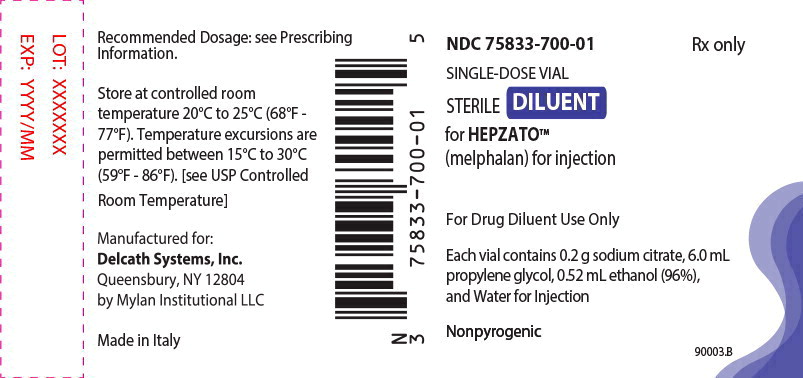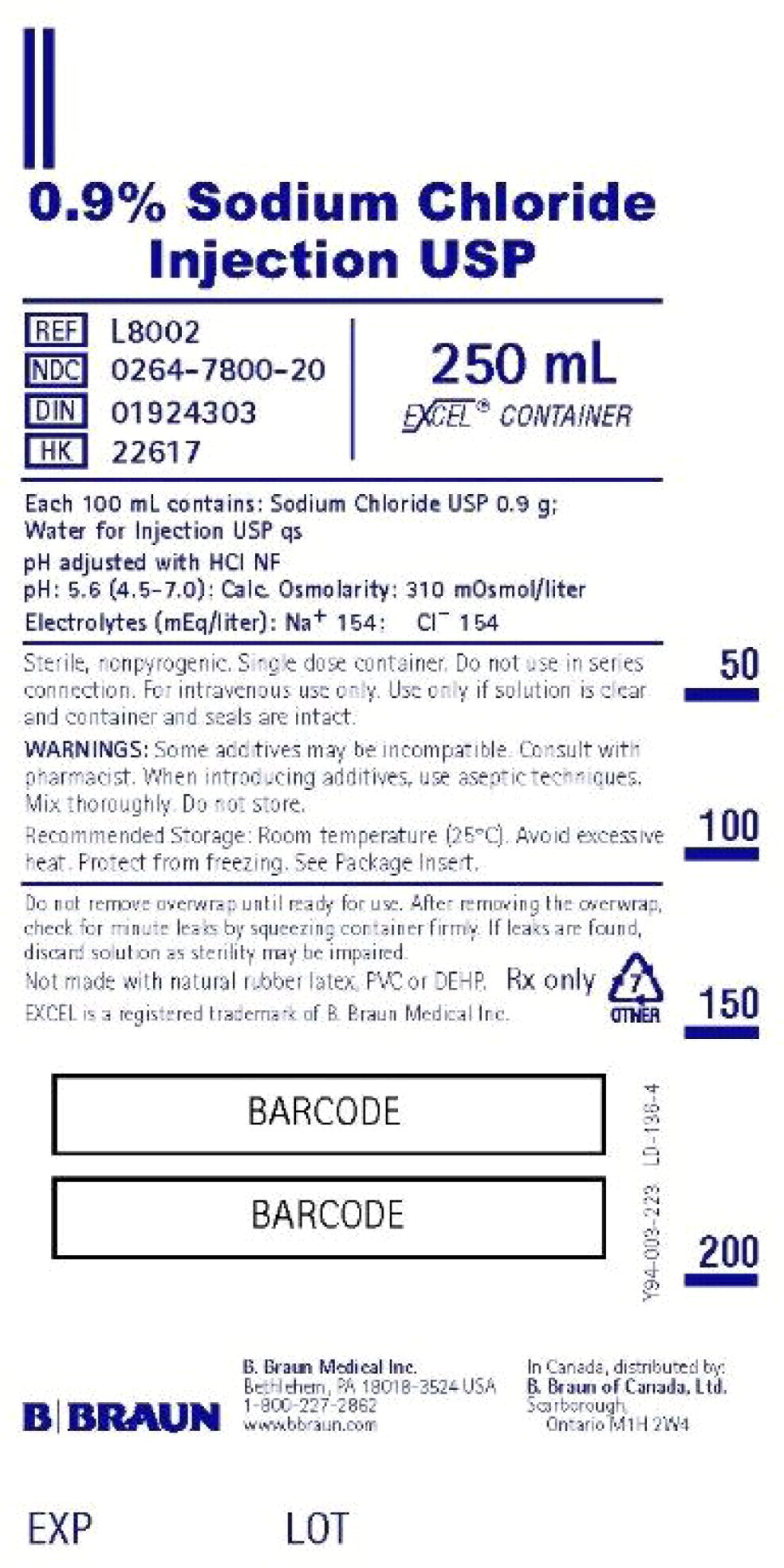 DRUG LABEL: Hepzato Kit
NDC: 75833-601 | Form: KIT | Route: INTRA-ARTERIAL
Manufacturer: Delcath Systems, Inc.
Category: prescription | Type: HUMAN PRESCRIPTION DRUG LABEL
Date: 20250519

ACTIVE INGREDIENTS: Melphalan Hydrochloride 50 mg/10 mL; Sodium Chloride 0.9 mg/100 mL
INACTIVE INGREDIENTS: Povidone, Unspecified; Sodium Citrate; Propylene Glycol; Alcohol; Water; Water; Hydrochloric Acid

HIGHLIGHTS OF PRESCRIBING INFORMATION

These highlights do not include all the information needed to use HEPZATO safely and effectively. See full prescribing information for HEPZATO KIT and HEPZATO KIT Hepatic Delivery System Instructions for Use.
HEPZATO (melphalan) for injection is a component of the HEPZATO KIT Hepatic Delivery System (HDS) for intra-arterial use.
Initial U.S. Approval: 1964

WARNING: PERI-PROCEDURAL COMPLICATIONS, MYELOSUPPRESSION

WARNING: SEVERE PERI-PROCEDURAL COMPLICATIONS, MYELOSUPPRESSION

See full prescribing information for complete boxed warning.

- Severe peri-procedural complications including hemorrhage, hepatocellular injury, and thromboembolic events may occur with intra-hepatic administration of HEPZATO. Assess patients for these adverse reactions during and for 72 hours following administration of HEPZATO. (5.1)
- HEPZATO is available only through a restricted program under a Risk Evaluation and Mitigation Strategy called the HEPZATO KIT REMS. (5.2)
- Myelosuppression with resulting severe infection, bleeding, or symptomatic anemia may occur with HEPZATO. Monitor hematologic laboratory parameters and delay additional cycles of HEPZATO therapy until blood counts have improved.(5.3)

1 INDICATIONS AND USAGE

HEPZATO is an alkylating drug indicated as a liver-directed treatment for adult patients with uveal melanoma with unresectable hepatic metastases affecting less than 50% of the liver and no extrahepatic disease, or extrahepatic disease limited to the bone, lymph nodes, subcutaneous tissues, or lung that is amenable to resection or radiation.(1)

2 DOSAGE AND ADMINISTRATION

HEPZATO, a component of the HEPZATO KIT, is administered by intra-arterial infusion into the hepatic artery (see instructions for use [IFU]). The recommended dose is 3 mg/kg based on ideal body weight (see Table 1), with a maximum absolute dose of 220 mg during a single HEPZATO treatment. (2.2). The drug is infused over 30 minutes followed by a 30-minute washout period (see IFU). Treatments should be administered every six (6) to eight (8) weeks but can be delayed until recovery from toxicities and as per clinical judgement. (2.3)

3 DOSAGE FORMS AND STRENGTHS

For injection: HEPZATO includes 50 mg freeze-dried (lyophilized) melphalan powder per vial in five (5) single dose vials, intended for reconstitution with the supplied diluents. (3)

4 CONTRAINDICATIONS

- Active intracranial metastases or brain lesions with a propensity to bleed
- Liver failure, portal hypertension, or known varices at risk for bleeding
- Surgery or medical treatment of the liver in the previous 4 weeks
- Active cardiac conditions including, but not limited to, unstable coronary syndromes (unstable or severe angina or myocardial infarction), worsening or new-onset congestive heart failure, significant arrhythmias, or severe valvular disease
- History of allergies or known hypersensitivity to melphalan or a component or material utilized within the HEPZATO KIT including natural rubber latex, heparin, and severe hypersensitivity to iodinated contrast not controlled by antihistamines and steroids (4)

5 WARNINGS AND PRECAUTIONS

- Hypersensitivity reactions, including anaphylaxis, have occurred in patients who received an intravenous (IV) formulation of melphalan. Immediately terminate hepatic arterial melphalan infusion for hypersensitivity reactions and administer supportive care. (5.4)
- Gastrointestinal disturbances such as nausea and vomiting, abdominal pain and diarrhea are common. (5.5)
- Carcinogenic/Mutagenic effects: Secondary malignancies, including acute nonlymphocytic leukemia, myeloproliferative syndrome, and carcinoma, have been reported in patients with cancer treated with alkylating drugs (including melphalan). Melphalan has been shown to cause chromatid or chromosome damage in humans. (5.6)
- Embryo-fetal toxicity: Can cause fetal harm. Advise females of reproductive potential and males with female partners of reproductive potential of the potential risk to a fetus and to use effective contraception. (5.7, 8.1, 8.3)
- Infertility: Melphalan-based chemotherapy regimens have been reported to cause suppression of ovarian function in premenopausal women and testicular suppression in men. (5.8)

6 ADVERSE REACTIONS

Most common (≥20%) adverse reactions or laboratory abnormalities are thrombocytopenia, fatigue, anemia, nausea, musculoskeletal pain, leukopenia, abdominal pain, neutropenia, vomiting, increased alanine aminotransferase, prolonged activated partial thromboplastin time, increased aspartate aminotransferase, increased alkaline phosphatase, and dyspnea.

To report SUSPECTED ADVERSE REACTIONS, contact Delcath at 1-833-632-0458 and www.Delcath.com or FDA at 1-800-FDA-1088 or http://www.fda.gov/medwatch.

8 USE IN SPECIFIC POPULATIONS

- HEPZATO should not be used in patients < 35 kg. (2.2)
- Lactation: Advise not to breastfeed (8.2)

FULL PRESCRIBING INFORMATION

WARNING: PERI-PROCEDURAL COMPLICATIONS, MYELOSUPPRESSION

- Severe peri-procedural complications including hemorrhage, hepatocellular injury, and thromboembolic events may occur via hepatic intra-arterial administration of HEPZATO. Assess patients for these adverse reactions during and for at least 72 hours following administration of HEPZATO [see Warnings and Precautions (5.1)].
- HEPZATO is available only through a restricted program under a Risk Evaluation and Mitigation Strategy called the HEPZATO KIT REMS [see Warnings and Precautions (5.2)].
- Myelosuppression with resulting severe infection, bleeding, or symptomatic anemia may occur with HEPZATO. Monitor hematologic laboratory parameters and delay additional cycles of HEPZATO therapy until blood counts have improved. [see Warnings and Precautions (5.1)]

1 INDICATIONS AND USAGE

HEPZATO for injection, as a component of the HEPZATO KIT, is indicated as a liver-directed treatment for adult patients with uveal melanoma with unresectable hepatic metastases affecting less than 50% of the liver and no extrahepatic disease or extrahepatic disease limited to the bone, lymph nodes, subcutaneous tissues, or lung that is amenable to resection or radiation.

2 DOSAGE AND ADMINISTRATION

2.1 Important Pre-Treatment and Administration Information

HEPZATO is a component of the HEPZATO KIT Hepatic Delivery System [HDS]. Refer to the HEPZATO KIT Hepatic Delivery System Instructions for Use (IFU) for additional instructions including pre-infusion evaluation, hydration, premedication, anticoagulation, and supportive care.

Caution: The double balloon catheter component of the HDS contains natural rubber latex which may cause allergic reactions [see Contraindications (4)].

- Healthcare providers must complete the required HEPZATO KIT REMS training prior to administration of the HEPZATO KIT [see Warnings and Precautions (5.2)].
- Discontinue oral anticoagulation and drugs affecting platelet function prior to the procedure [see Warnings and Precautions (5.1)].
- Discontinue ACE-inhibitors, calcium channel blockers, or alpha-1-adrenergic blockers prior to the procedure [see Warnings and Precautions (5.1)].
- Conduct baseline hematologic testing. Administer intra-hepatic HEPZATO with the HEPZATO KIT only to patients with the following [see Warnings and Precautions (5.3)].
  - Hemoglobin ≥ 10 g/dL
  - Platelets ≥ 100,000/microliter
  - Neutrophils > 2000/microliter

2.2 Recommended Dosage

- Administer HEPZATO via the HEPZATO KIT Hepatic Delivery System only to patients weighing 35 kg or greater due to potential size limitations with respect to percutaneous catheterization.
- HEPZATO, a component of the HEPZATO KIT, is administered by infusion into the hepatic artery (see IFU) every 6 to 8 weeks for up to 6 total infusions.
- The recommended HEPZATO dose is 3 mg/kg based on ideal body weight (IBW), as calculated per Table 1 below, with a maximum of 220 mg during a single treatment.

Table 1: Calculation of IBW for HEPZATO Dosing
 | Height | Ideal Body Weight
Men | ≥ 152 cm | 52 kg + (0.75 kg/cm of height greater than 152 cm)
Men | < 152 cm | 52 kg – (0.75 kg/cm of height less than 152 cm)
Women | ≥ 152 cm | 49 kg + (0.67 kg/cm of height greater than 152 cm)
Women | < 152 cm | 49 kg – (0.67 kg/cm of height less than 152 cm)

2.3 Dosage Modifications for Adverse Reactions

A dosage reduction to 2 mg/kg is recommended for subsequent treatments for the following reasons:

- Grade 4 neutropenia of > 5 days duration despite growth factor support or associated with neutropenic fever;
- Grade 4 thrombocytopenia of > 5 days duration or associated with a hemorrhage that required a transfusion;

HEPZATO administered with the HEPZATO KIT should be discontinued if patients have life threatening or HEPZATO-related persistent toxicity that has not resolved to Grade 2 or less by 8 weeks following treatment.

2.4 Preparation and Administration

Refer to the HEPZATO KIT Hepatic Delivery System IFU for further details and instructions.

Reconstitute and dilute melphalan immediately prior to beginning intra-arterial infusion.

Reconstituted and diluted solutions of HEPZATO are unstable. No more than 60 minutes should elapse from reconstitution and completion of the intra-hepatic infusion of the diluted HEPZATO solution. A citrate derivative of melphalan has been detected in reconstituted HEPZATO in 30 minutes, and nearly 1% of labeled strength of melphalan hydrolyzes every 10 minutes when reconstituted HEPZATO is further diluted in 0.9% Sodium Chloride. A precipitate forms if the reconstituted solution is stored at 5°C. Do not refrigerate HEPZATO once reconstituted.

HEPZATO is a hazardous drug^1. Follow applicable special handling and disposal procedures.

Reconstitution and Dilution Instructions:

1. Rapidly (in 5 seconds or less) inject 10 mL of the supplied sterile diluent [see Dosage Forms and Strengths (3.0)] into the HEPZATO 50 mg vial using a sterile needle (20-gauge or larger) and syringe. The resulting solution will contain melphalan 5 mg/mL
2. Immediately shake the vial vigorously until a clear solution is obtained. No more than five (5) seconds should elapse between the discharge of the syringe and the commencement of shaking.
3. Immediately further dilute the required dose with the provided 0.9% sodium chloride injection, United States Pharmacopeia (USP), to a concentration not greater than 0.45 mg/mL, as follows
  - HEPZATO doses up to 110 mg:
    Dilute in 250 mL of 0.9% sodium chloride injection
  - HEPZATO doses 111 mg to 220 mg:
    Divide the total dose equally into 2 and dilute each in 250 mL of 0.9% sodium chloride injection (for example, if the total dose is 200 mg, dilute 100 mg in each 250 mL 0.9% sodium chloride injection)
4. Visually inspect parenteral drug products for particulate matter and discoloration prior to administration, whenever solution and container permit. If particulates and discolorations are noted, the product should not be used.
5. Administer diluted HEPZATO intra-arterially as described in the IFU. Complete the infusion within 30 minutes, followed by a 30-minute washout period. Refer to the IFU for additional administration procedures.

3 DOSAGE FORMS AND STRENGTHS

HEPZATO (melphalan) is supplied in the HEPZATO KIT that contains the following:

- Melphalan for injection: 5 single dose, clear glass vials for injection, containing 50 mg white to pale yellow lyophilized powder, intended for reconstitution with the supplied diluents

4 CONTRAINDICATIONS

HEPZATO and the HEPZATO KIT are contraindicated in patients with:

- Active intracranial metastases or brain lesions with a propensity to bleed
- Liver failure, portal hypertension, or known varices at risk for bleeding
- Surgery or medical treatment of the liver in the previous 4 weeks
- Uncorrectable coagulopathy
- Inability to safely undergo general anesthesia, including active cardiac conditions including, but not limited to, unstable coronary syndromes (unstable or severe angina or myocardial infarction), worsening or new-onset congestive heart failure, significant arrhythmias, or severe valvular disease
- History of allergies or known hypersensitivity to melphalan
- History of allergies or known hypersensitivity to a component or material utilized within the HEPZATO KIT including
  - History of allergy to natural rubber latex
  - History of allergy or hypersensitivity to heparin or presence of heparin-induced thrombocytopenia (HIT)
  - History of severe allergic reaction to iodinated contrast not controlled by premedication with antihistamines and steroids

5 WARNINGS AND PRECAUTIONS

5.1 Peri-Procedural Complications

Hemorrhage, hepatocellular injury, and thromboembolic events have been observed when HEPZATO has been administered via hepatic intra-arterial administration. Administration of HEPZATO requires general anesthesia and extracorporeal bypass of circulation which may cause life threatening or fatal adverse effects. Ensure the patient is euvolemic but do not overhydrate the patient. Monitor for these peri-procedural complications during the procedure and for at least 72 hours following the procedure.

To mitigate the risk of thromboembolic events, administer anticoagulation as described in the IFU during the procedure.

Due to the risk of bleeding, do not use in patients with uncorrectable coagulopathies and delay treatment with the HEPZATO KIT for at least 4 weeks after surgery or other medical procedure involving the liver. Platelets and clotting factors may be removed during the HEPZATO KIT procedure. Monitor platelets and coagulation parameters as described in the IFU. If life-threatening bleeding occurs during the procedure, reverse anticoagulation as described in the IFU and correct coagulopathy as appropriate. Discontinue anticoagulation with warfarin or other oral anticoagulants prior to the procedure; resume when hemostasis has been restored after the procedure, provided no bleeding complications have been observed. Refer to the Prescribing Information of the anticoagulant agent for bridging recommendations for anti-coagulation prior to surgical procedures. Discontinue drugs affecting platelet function such as aspirin, non-steroidal anti-inflammatory drugs, or other anti-platelet drugs one week before the procedure.

Patients with abnormal hepatic vascular (especially arterial supply) or biliary (especially re-implantation of bile duct) anatomy or gastric acid hypersecretion syndromes may be at increased risk of peri-procedural complications or other severe adverse reactions. Screen patients for a history of prior surgeries involving the bile duct to assess whether the patient is an appropriate candidate for HEPZATO KIT and monitor patients for adverse reactions following HEPZATO KIT administration.

Procedure-related reductions in blood pressure including severe hypotension can occur during the HEPZATO KIT procedure. Closely monitor blood pressure during the procedure. Patients may require fluid support and vasopressors. To reduce the risk of severe hypotension, assess hypothalamic-pituitary-adrenal axis function, and temporarily discontinue ACE-inhibitors, calcium channel blockers, or alpha-1-adrenergic blockers for at least 5 half-lives prior to treatment with the HEPZATO-KIT. If necessary, use other short-acting antihypertensive drugs to manage blood pressure during the peri-procedure period.

5.2 HEPZATO KIT REMS PROGRAM

The HEPZATO KIT is only available through a restricted program under a REMS, because of the risk of severe peri-procedural complications including hemorrhage, hepatocellular injury, and thromboembolic events defined in the REMS. The HEPZATO KIT should only be used by trained healthcare providers [see Warnings and Precautions (5.1)].

Important requirements of the HEPZATO KIT REMS include:

- Healthcare settings that dispense and administer HEPZATO KIT must be enrolled, certified, and comply with the REMS requirements.
- Certified healthcare facilities must ensure that healthcare providers who perform the Percutaneous Hepatic Perfusion (PHP) procedure are trained on the use of HEPZATO KIT and must only dispense HEPZATO when authorized to do so by the REMS.
- Certified healthcare facilities must ensure that patients are assessed for severe peri-procedural complications during the procedure and for at least 72 hours following the procedure.

Further information is available at www.HEPZATOKITREMS.com or contact Delcath Systems at 1-833-632-0457.

5.3 Myelosuppression

Hematologic adverse reactions, including thrombocytopenia, anemia, and neutropenia have been reported in patients treated with HEPZATO. The risk of hematologic adverse reactions may be increased in patients who have received prior chemotherapy, bone irradiation, or who have compromised bone marrow function.

In the 95 patients who received HEPZATO in the FOCUS trial, 68% had Grade 3 or 4 myelosuppression. A total of 55%, 33%, and 30% experienced Grade 3 or 4 thrombocytopenia, anemia, and neutropenia, respectively. Median time to thrombocyte nadir was 13 days (range: 3-33) after treatment with median recovery in 20 days (range: 4-29) after treatment. Median time to hemoglobin nadir was 10 days (range: 3-21) after treatment with median recovery in 13 days (range: 4-28) after treatment. Median time to neutrophil nadir was 11 days (range: 3-36) after treatment with median recovery in 17 days (range: 9-36) after treatment.

Monitor patients for severe infections, bleeding, and symptomatic anemia. Only administer HEPZATO in patients with platelets >100,000/microliter, hemoglobin ≥10.0 gm/dL and neutrophils >2,000/microliter. Administer transfusions or growth factors as appropriate [see Dosage and Administration (2.1)].

5.4 Hypersensitivity Reactions

Hypersensitivity reactions, including anaphylaxis, have occurred in approximately 2% of patients who received an intravenous (IV) formulation of melphalan. These reactions with melphalan are characterized by urticaria, pruritus, edema, skin rashes, and in some patients, tachycardia, bronchospasm, dyspnea, and hypotension. Hypersensitivity can occur in patients with or without prior exposure to IV or oral melphalan.

When a hypersensitivity reaction is observed, immediately terminate the hepatic arterial HEPZATO infusion and administer necessary supportive care [see Contraindications (4)].

Patients with a history of allergic reactions to iodinated contrast may experience hypersensitivity reactions, including anaphylaxis, during treatment with the HEPZATO KIT. Premedicate patients with a history of allergic reaction to iodinated contrast prior to treatment with HEPZATO KIT. Do not administer HEPZATO KIT in patients with a history of severe allergic reactions or anaphylaxis to iodinated contrast [see IFU, see Contraindications (4)].

5.5 Gastrointestinal Adverse Reactions

Gastrointestinal adverse reactions including nausea and vomiting, abdominal pain, and diarrhea are common, and occurred in 84% of patients treated with HEPZATO in the FOCUS trial. Administer a proton pump inhibitor the day prior to and the morning of the procedure. If anti-emetic treatment is required, pre-medicate with anti-emetic therapy in subsequent cycles.

5.6 Secondary Malignancies

Melphalan has been shown to cause chromatid or chromosome damage in humans. Secondary malignancies, including acute nonlymphocytic leukemia, myeloproliferative syndrome, and carcinoma, have been reported in patients with cancer treated with intravenous alkylating drugs including melphalan. Some patients also received other chemotherapeutic agents or radiation therapy. Precise quantification of the risk of acute leukemia, myeloproliferative syndrome, or carcinoma is not possible. Published reports of leukemia in patients who have received oral or IV melphalan (and other alkylating drugs) suggest that the risk of leukemogenesis increases with chronicity of treatment and with cumulative dose [see Nonclinical Toxicology (13.1)].

5.7 Embryo-Fetal Toxicity

Based on animal studies and its mechanism of action, melphalan can cause fetal harm when administered to a pregnant woman. Melphalan is genotoxic, targets actively dividing cells, and was embryolethal and teratogenic in rats. Advise pregnant women of the potential risk to a fetus. Advise females of reproductive potential to use effective contraception during treatment with HEPZATO and for 6 months after the last dose. Advise males with female partners of reproductive potential to use effective contraception during treatment with HEPZATO and for 3 months after the last dose [see Use in Specific Populations (8.1, 8.3), Nonclinical Toxicology (13.1)].

5.8 Infertility

Melphalan-based chemotherapy regimens have been reported to cause suppression of ovarian function in premenopausal women, resulting in persistent amenorrhea in approximately 9% of patients. Reversible or irreversible testicular suppression has also been reported [see Use in Specific Populations (8.3)].

6 ADVERSE REACTIONS

Below are adverse reactions associated with HEPZATO KIT. Additional adverse reactions related to the procedure and/or medical device are described in further detail in the HEPZATO KIT IFU. The following clinically significant adverse reactions are described elsewhere in the labeling:

- Peri-procedural complications [see Warnings and Precautions (5.1)]
- Myelosuppression [see Warnings and Precautions (5.3)]
- Hypersensitivity Reactions [see Warnings and Precautions (5.4)]
- Gastrointestinal Adverse Reactions [see Warnings and Precautions (5.5)]
- Secondary Malignancies [see Warnings and Precautions (5.6)]

6.1 Clinical Trials Experience

Because clinical trials are conducted under widely varying conditions, adverse reaction rates observed in the clinical trials of a drug-device combination cannot be directly compared to rates in the clinical trials of another drug and may not reflect the rates observed in practice.

The adverse drug reactions (ADRs) described in this section were identified from the FOCUS trial. FOCUS was a multicenter trial that evaluated HEPZATO (melphalan) administered via the HEPZATO KIT in patients with unresectable hepatic metastases from uveal melanoma. In the FOCUS trial, a total of 95 patients were enrolled into the HEPZATO KIT arm, of which 91 patients received treatment with HEPZATO.

Serious adverse reactions occurred in 45% of patients who received HEPZATO. Serious adverse reactions occurring in ≥ 2% of patients were thrombocytopenia (10%), neutropenia (8%), febrile neutropenia (7%), platelet count decreased (6%), leukopenia (4.2%), cardiac arrest (3.2%), neutrophil count decreased (2.1%), hypoxia (2.1%), pleural effusion (2.1%), pulmonary edema (2.1%), and deep vein thrombosis (2.1%). Fatal adverse reactions occurred in 3 (3.2%) patients who were treated with HEPZATO; these included cardiac arrest, acute hepatic failure and bacterial peritonitis.

HEPZATO was permanently discontinued due to adverse reactions in 18% of patients with neutropenia being the most common adverse reaction (3.2%) requiring permanent discontinuation.

Dose reductions due to an adverse reaction occurred in 14% of patients who received HEPZATO. Adverse reactions which required dose reductions occurring in ≥ 2% of patients were platelet count decreased (6%), neutropenia (4.2%), anemia (2.1%), and thrombocytopenia (2.1%).

Adverse reactions that required dosage interruption in ≥ 2% of patients who received HEPZATO were platelet count decreased (6%), neutropenia (5%), thrombocytopenia (3.2%), anemia (3.2%) and febrile neutropenia (2.1%).

The most common (≥20%) adverse reactions or laboratory abnormalities reported in patients treated with HEPZATO were thrombocytopenia (65%), fatigue (65%), anemia (63%), nausea (57%), musculoskeletal pain (46%), leukopenia (46%), abdominal pain (39%), neutropenia (35%), vomiting (35%), increased alanine aminotransferase (32%), prolonged activated partial thromboplastin time (28%), increased aspartate aminotransferase (28%), increased blood alkaline phosphatase (27%), and dyspnea (23%).

Table 2 and Table 3 summarize adverse reactions and laboratory abnormalities, respectively, that occurred in FOCUS.

Table 2 All Adverse Reactions Observed at a Frequency of >10% in Patients Treated with HEPZATO
 | All Adverse Reactions N=95
 | All Grades (%) | Grades 3 or 4 (%)
Gastrointestinal disorders
Nausea | 57 | 0
Abdominal Pain^1 | 39 | 1
Vomiting^1 | 35 | 0
Diarrhea^1 | 17 | 1
General disorders
Fatigue^1 | 65 | 0
Pyrexia^1 | 16 | 0
Musculoskeletal And Connective Tissue Disorders
Musculoskeletal Pain^1 | 46 | 1
Groin Pain | 11 | 0
Respiratory disorders
Dyspnea^1 | 23 | 2
Cough^1 | 15 | 0
Nervous system disorders
Headache^1 | 19 | 0
Lethargy | 12 | 0
Dizziness^1 | 11 | 0
Injury and procedural complications
Contusion | 17 | 0
Metabolism and nutrition disorders
Decreased appetite | 16 | 0
Vascular disorders
Hemorrhage^1 | 15 | 1
Hypotension^1 | 13 | 3
^1Represents a composite of multiple, related preferred terms

Table 3: Laboratory Abnormalities Observed at a Frequency of >10% in Patients Treated with HEPZATO
Laboratory Abnormality | All Laboratory Abnormalities N=95
 | All Grades (%) | Grades 3 or 4 (%)
Platelets decreaseda | 65 | 55
Hemoglobin decreaseda | 63 | 33
Leukocytes decreaseda | 46 | 34
Neutrophils decreaseda | 35 | 30
Alanine aminotransferase increased | 32 | 3
International normalized ratio increased | 31 | 8
Activated partial thromboplastin time prolonged | 28 | 8
Aspartate aminotransferase increased | 28 | 4
Blood alkaline phosphatase increased | 27 | 2
Calcium decreased | 13 | 3
Troponin I increased | 13 | 2
Blood bilirubin increased | 11 | 3
a Represents a composite of multiple, related preferred terms

8 USE IN SPECIFIC POPULATIONS

8.1 Pregnancy

Risk Summary

Based on animal studies and its mechanism of action, melphalan can cause fetal harm when administered to a pregnant woman, including teratogenicity and/or embryo-fetal lethality [see Clinical Pharmacology (12.1)]. Melphalan is a genotoxic drug and can cause chromatid or chromosome damage in humans [see Nonclinical Toxicology (13.1)]. In animal studies, melphalan was embryolethal and teratogenic in rats at doses below the recommended clinical doses [see Data]. Advise a pregnant woman of the potential risk to a fetus.

The background risk of major birth defects and miscarriage for the indicated populations are unknown. However, the background risk in the United States general population of major birth defects is 2% to 4% and of miscarriage is 15% to 20% of clinically recognized pregnancies.

Data

Animal Data

Adequate animal studies have not been conducted with IV melphalan. Melphalan was embryolethal and teratogenic in rats following oral administration of 6 to 18 mg/m^2/day for ten (10) days (0.05 to 0.16 times the recommended clinical dose of 3 mg/kg or 111 mg/m^2/day) and intraperitoneal administration of 18 mg/m^2 (0.16 times the highest recommended clinical dose). Malformations resulting from melphalan administration included alterations of the brain (underdevelopment, deformation, meningocele, and encephalocele) and eye (anophthalmia and microphthalmos), reduction of the mandible and tail, and hepatocele (exomphaly).

8.2 Lactation

Risk Summary

It is not known whether melphalan is present in human milk. Because many drugs are excreted in human milk and because of the potential for serious adverse reactions in nursing children from melphalan, breastfeeding is not recommended during treatment with melphalan and for one week after the last dose.

8.3 Females and Males of Reproductive Potential

Melphalan can cause fetal harm when administered to a pregnant woman. Verify the pregnancy status of females of reproductive potential prior to initiating HEPZATO [see Use in Specific Populations (8.1)].

Contraception

Females

Advise females of reproductive potential to use effective contraception during treatment with HEPZATO and for 6 months after the last dose.

Males

HEPZATO administration may damage spermatozoa and testicular tissue, resulting in possible genetic fetal abnormalities. Advise males with female partners of reproductive potential to use effective contraception during treatment with HEPZATO and for 3 months after the last dose [see Nonclinical Toxicology (13.1)].

Infertility

Females

Melphalan causes suppression of ovarian function in premenopausal women, resulting in amenorrhea in a significant number of patients.

Males

Reversible and irreversible testicular suppression has been reported in male patients after administration of melphalan.

8.4 Pediatric Use

The safety and effectiveness in pediatric patients have not been established.

8.5 Geriatric Use

Clinical studies of HEPZATO did not include sufficient numbers of subjects aged 65 and over to determine whether they respond differently from younger subjects. In the FOCUS trial, 30 of the 91 patients (33%) were 65 years and older.

10 OVERDOSE

No information on melphalan overdosage is available following administration of HEPZATO. Overdoses resulting in death have been reported following treatment with high intravenous (IV) doses of melphalan.

Overdoses via the IV route, including doses up to 290 mg/m^2 (approximately 7.5 mg/kg IBW), have produced the following symptoms: severe nausea and vomiting, decreased consciousness, convulsions, muscular paralysis, and cholinomimetic effects. Severe mucositis, stomatitis, colitis, diarrhea, and hemorrhage of the gastrointestinal tract occur at high IV doses (>100 mg/m^2 or approximately 2.6 mg/kg IBW). Elevations in liver enzymes and veno-occlusive disease occur infrequently. Significant hyponatremia caused by an associated inappropriate secretion of antidiuretic hormone syndrome has been observed. Nephrotoxicity and adult respiratory distress syndrome have been reported.

The principal toxic effect is bone marrow suppression. Hematologic parameters should be closely followed for three (3) to six (6) weeks. General supportive measures together with appropriate blood transfusions and antibiotics should be instituted as deemed necessary by the physician. General supportive measures, together with appropriate blood and platelet transfusions, should be instituted if necessary and consideration given to hospitalization, antibiotic cover, and the use of hematological growth factors.

This drug is not removed from systemic plasma to any significant degree by hemodialysis or hemoperfusion.

11 DESCRIPTION

Melphalan, is a bifunctional alkylating drug that is active against selected human neoplastic diseases. Melphalan is available as melphalan hydrochloride salt. The chemical name of melphalan hydrochloride is 4-[bis(2-chloroethyl)amino]-L-phenylalanine hydrochloride. The molecular formula is C13H18Cl2N2O2.HCl and the molecular weight is 341.67.

Melphalan is practically insoluble in water and has a pKa1 of ~2.5.

HEPZATO, for injection, is supplied as a sterile, nonpyrogenic, freeze-dried white to pale yellow freeze-dried cake/ powder. Each single dose vial contains melphalan 50 mg, equivalent to 56 mg of melphalan hydrochloride and 20 mg povidone.

HEPZATO (melphalan) is reconstituted using the sterile diluent provided. Each vial of sterile diluent contains sodium citrate 0.2 g, propylene glycol 6.0 mL, ethanol (96%) 0.52 mL, and water for injection to a total of 10 mL.

HEPZATO (melphalan) for use with the hepatic delivery system is administered intra-arterially.

12 CLINICAL PHARMACOLOGY

12.1 Mechanism of Action

Melphalan is an alkylating drug of the bischloroethylamine type. As a result, its cytotoxicity appears to be related to the extent of its interstrand cross-linking with DNA, probably by binding at the N7 position of guanine. It is active against both resting and rapidly dividing tumor cells.

12.2 Pharmacodynamics

Exposure-Response

Melphalan exposure-response relationships and the time course of pharmacodynamic response following administration of HEPZATO via the Hepatic Delivery System are not fully characterized.

12.3 Pharmacokinetics

Geometric mean of systemic melphalan maximum concentration (Cmax) is 2.4 (%CV 3.0) mcg/mL and the AUC0-last was 1.8 (%CV 1.1) mcg*hr/mL.

The melphalan median (range) time to Cmax (Tmax) is 0.57 (0.05 – 1.18) hours following administration of HEPZATO.

Distribution

The melphalan plasma protein binding is approximately 78% following administration of HEPZATO. Serum albumin accounts for approximately 40% to 60% and α1-acid glycoprotein approximately 20% of the plasma protein binding.

Elimination

The median terminal elimination phase half-life of 1.07 hours that is consistent with IV melphalan administration.

Metabolism:

Melphalan is primarily metabolized by hydrolysis to inactive metabolites.

Excretion:

Liver uptake and removal of melphalan by isolation of hepatic venous blood and subsequent filtration by HDS are the two main processes for reducing the amount of melphalan that is available systemically following administration of HEPZATO. HDS reduced systemic melphalan exposure with a mean (SD) filter efficiency of 82.7% (14.4%) for the total filtration period.

Systemic melphalan is eliminated by renal excretion of parent drug and metabolites.

Specific Populations

No clinically significant differences in the pharmacokinetics of melphalan were observed based on body weight (43 - 150 kg), creatinine clearance (> 50 mL/min), or hepatic parameters (ALT (7 - 157 IU/L), AST (11 - 90 IU/L), or bilirubin (0.06 - 1.5 mg/dL) following administration of HEPZATO KIT.

13 NONCLINICAL TOXICOLOGY

13.1 Carcinogenesis, Mutagenesis, Impairment of Fertility

Adequate and well-controlled carcinogenicity studies have not been conducted in animals. However, intraperitoneal (IP) administration of melphalan in rats (5.4 to 10.8 mg/m^2) and in mice (2.25 to 4.5 mg/m^2) 3 times per week for 6 months followed by 12 months post-dose observation produced peritoneal sarcoma and lung tumors, respectively.

Intramuscular administration of melphalan at 6 and 60 mg/m^2 produced structural aberrations of the chromatid and chromosomes in bone marrow cells of Wistar rats.

14 CLINICAL STUDIES

Study in Patients with Uveal Melanoma

The efficacy of HEPZATO in hepatic-dominant metastatic uveal melanoma was based on the results from 91 patients who received HEPZATO via the HEPZATO KIT in the FOCUS Study (NCT02678572), a multicenter, open-label trial. To be eligible for enrollment, patients were required to have metastatic uveal melanoma with metastases predominately involving the liver (liver dominant). Limited extrahepatic disease in the bone, subcutaneous sites, lymph nodes, or lung was permitted if the life-threatening component of the uveal melanoma was in the liver and the extrahepatic disease was amenable to resection or radiation and had a defined treatment plan. Patients with metastases in more ≥ 50% of the liver parenchyma, unable to undergo general anesthesia, ECOG ≥2, platelets < 100,000/microliter, absolute neutrophil count < 1,500/microliter, hemoglobin < 10 gm/dL, Child-Pugh Class B or C cirrhosis, or hepatitis B or C infection were excluded.

Patients received 3 mg/kg of melphalan based on ideal body weight (IBW, maximum total dose of 220 mg) administered intraarterially using the Hepatic Delivery System (HDS) every 6-8 weeks for up to 6 infusions. The median number of infusions administered per patient was 4 (range: 1-6). Thirty-seven percent (37%) of the 91 patients treated received the maximum of six infusions of treatment.

The major efficacy outcome measures were objective response rate (ORR) and duration of response (DoR) using computed tomography (CT) or magnetic resonance imaging (MRI) assessed by an independent central review committee (IRC) using Response Evaluation Criteria in Solid Tumors (RECIST) v1.1.

The median age of patients was 61 years (range 20 to 78), 52% were female, 95% were White, 5% unavailable, and all patients had Eastern Cooperative Oncology Group (ECOG) performance status of 0 or 1. Ninety-five percent (95%) of enrolled patients had either 2 or 3 hepatic lesions. Seventy-nine percent (79%) of patients had <25% liver involvement. Thirty percent of the treated patients had extra-hepatic lesions, of which 20% had 1 extrahepatic lesion and 10% had 2 or more; overall 12% of patients had lung, 11% soft tissue/subcutaneous, 5% lymph node, and 4% had bone involvement. Forty-three percent (43%) of patients underwent prior therapy for metastatic disease, including systemic therapy (25%), other surgeries or procedures (14%), and radiation (11%).

The efficacy results of HEPZATO treatment are summarized in Table 4.

Table 4 Efficacy Results for Patients in FOCUS Trial
 | HEPZATO (N=91)
Objective Response Rate
ORR (95% CI)^1 | 36.3% (26.4, 47.0)
Complete Response | 7.7%
Partial Response | 28.6%
Duration of response (months)
Number of Responders | n= 33
Median^2 (months) (95% CI)^3 | 14.0 (8.3, 17.7)
% Responder with DoR≥6 months^4 | 70 %
% Responder with DoR≥12 months^4 | 30 %
^1 Clopper-Pearson method ^2 Kaplan Meier method ^3 Brookmeyer and Crowley method ^4 Based on observed duration of response

15 REFERENCES

^1OSHA Hazardous Drugs. OSHA. http://www.osha.gov/hazardous-drugs

16 HOW SUPPLIED/STORAGE AND HANDLING

How Supplied

The HEPZATO KIT includes the HEPZATO 5 x 5 Drug Pack and the Hepatic Delivery System (HDS). Each 5 x 5 HEPZATO KIT Drug Pack includes HEPZATO (melphalan) and diluents for reconstitution and dilution:

- Each vial of HEPZATO contains 50 mg melphalan for injection supplied as a sterile, nonpyrogenic, freeze-dried cake/powder in a carton containing 5 single-dose, glass vials (NDC 75833-800-01).
- Each vial of sterile diluent contains sodium citrate 0.2 g, propylene glycol 6.0 mL, ethanol (96%) 0.52 mL, and water for injection to a total of 10 mL in a carton containing 5 single-dose, glass vials for reconstitution (NDC 75833-700-01).
- Each of two 250 mL plastic containers of 0.9% sodium chloride injection USP (NDC 0264-7800-20).

HEPZATO (melphalan) for injection must only be administered with the HDS device supplied with the HEPZATO KIT and components specified by Delcath Systems, Inc, in the IFU [see Dosage and Administration (3)].

Storage and Handling

HEPZATO for injection and its associated diluents including 0.9% sodium chloride must be stored at controlled room temperature 20°C to 25°C (68°F to 77°F). Temperature excursions are permitted between 15°C- 30°C (59°F-86°F) [see USP Controlled Room Temperature].

The Hepatic Delivery System components may be stored at room temperature.

Melphalan is a hazardous drug. Follow applicable special handling and disposal procedures.^1

HEPZATO is light sensitive. Retain in original carton until use.

HEPZATO (melphalan) for injection

Manufactured for:
Delcath Systems, Inc.
Queensbury, NY 12804
by Mylan Institutional LLC
Made in Italy

HEPZATO KIT (melphalan for Injection/Hepatic Delivery System)

Packaged and Distributed by:
Delcath Systems, Inc.
Queensbury, NY 12804

17 Patient Counseling Information

Advise patients or their caregivers of the following risks of the HEPZATO KIT:

Peri-Procedural Complications

- Advise patients of the severe procedural risks associated with administration of melphalan using the HEPZATO KIT including hemorrhage, hepatic injury, and thromboembolic events.
- Advise patients that they will be monitored in a hospital setting following each treatment.
- Advise patients taking anti-coagulant and anti-hypertensive medications that these may need to be discontinued prior to treatment with HEPZATO KIT [see Warnings and Precautions (5.1)].

Myelosuppression

- Advise patients to immediately contact their healthcare provider for a fever, bruising, or bleeding. Advise patients of the need for monitoring of blood counts [see Warnings and Precautions (5.3)].

Hypersensitivity

- Inform patients of the signs and symptoms of hypersensitivity. Advise patients to immediately report symptoms of hypersensitivity [see Warnings and Precautions (5.4)].

Latex Allergy

- The double balloon catheter component of the HEPZATO KIT Hepatic Delivery System contains natural rubber latex which may cause allergic reactions in latex-sensitive individuals [see Contraindications (4)].

Gastrointestinal

- Advise patients to report symptoms of nausea, vomiting and diarrhea, so that appropriate antiemetic and/or antidiarrheal medications can be administered [see Warnings and Precautions (5.5)].

Secondary Malignancies

- Advise patients that treatment with HEPZATO has the potential long-term risk of secondary malignancy [see Warnings and Precautions (5.6)].

Embryo-Fetal Toxicity

- Advise pregnant women of the potential risk to a fetus [see Warnings and Precautions (5.7) and Use in Specific Populations (8.1)].
- Advise females of reproductive potential to use effective contraception during treatment with HEPZATO and for 6 months after the last dose. Advise females to contact their healthcare provider if they become pregnant, or if pregnancy is suspected, while taking HEPZATO [see Warnings and Precautions (5.7) and Use in Specific Populations (8.1, 8.3)].
- Advise males with female partners of reproductive potential to use effective contraception during treatment with HEPZATO and for 3 months after the last dose [see Use in Specific Populations (8.3)].

Lactation

- Advise women not to breastfeed during treatment with HEPZATO and for one week after the last dose [see Warnings and Precautions (5.7) and Use in Specific Populations (8.2)]

Infertility

- Inform both females and males of reproductive potential about the risk of infertility [see Warnings and Precautions (5.8) and Use in Specific Populations (8.3)].

HEPZATO (melphalan) for Injection

Manufactured for:
Delcath Systems, Inc.
Queensbury, NY 12804
by Mylan Institutional LLC
Made in Italy

HEPZATO KIT (melphalan for Injection/Hepatic Delivery System)

Packaged and Distributed by:
Delcath Systems, Inc.
Queensbury, NY 12804

© Copyright, 2023 Delcath Systems, Inc. All rights reserved.

120070.A

INSTRUCTIONS FOR USE

ASSEMBLED SYSTEM – FIGURE 1

SUPPLIED DISPOSABLE COMPONENTS – FIGURE 2

HEPZATO KIT™

HEPZATO (melphalan) for Injection/Hepatic Delivery System

COMPLETE REQUIRED REMS TRAINING BEFORE USING THIS DEVICE FOR THE FIRST TIME. ENSURE YOU COMPLETELY READ AND UNDERSTAND THE INSTRUCTIONS FOR USE.

DESCRIPTION OF SYSTEM COMPONENTS

HEPZATO KIT™ consists of a closed circuit of catheters and drug-specific filters utilized to deliver Hepzato (melphalan) to the hepatic artery and to lower the concentration of melphalan in the blood before it is returned to systemic circulation. A schematic overview of how the Hepatic Delivery System components work together is presented in Figure 1: Assembled System. The system is designed to be used with a Medtronic Bio-Console® 560 Speed Controller System and TX50P Flow Transducer.

1. Double Balloon Catheter (DBC) -- 16F (shaft) polyurethane double balloon catheter that is placed in the retro-hepatic inferior vena cava to isolate the hepatic venous blood and transport it to the Extracorporeal Hemofiltration Circuit for filtration. The catheter has one large (central) drainage lumen and four accessory ports. Due to variation in the length of a patient's retro-hepatic segment of the inferior vena cava and relative positions of hepatic and renal veins, the Double Balloon Catheter is available in two different balloon configurations: 50 mm or 62 mm between the two balloons.

Using pre-operative computed tomography (CT) imaging, or by performing an inferior vena cavogram prior to placement of the Double Balloon Catheter, estimate the length of the retro-hepatic segment of the inferior vena cava and the relative positions of hepatic and renal veins in order to determine the optimum Double Balloon Catheter balloon spacing: 50mm or 62mm.

Two of the accessory ports are used to inflate low-pressure occlusion balloons, which are inflated independently to occlude the inferior vena cava above and below the hepatic veins. When inflated, the cephalic (superior – blue port) balloon obstructs the inferior vena cava above the hepatic veins and the caudal (inferior – yellow port) balloon obstructs the inferior vena cava below the hepatic veins, thus isolating hepatic venous blood in the fenestrated segment between the balloons.

The large drainage lumen with a quick connect fitting is a conduit to the fenestrations between the two occlusion-balloons. The fenestrations allow the hepatic venous blood to flow into the drainage lumen and exit the catheter at the proximal end.

The third accessory (translucent) port labeled “CONTRAST” is for injections of iodinated contrast medium through the fenestrations, to check catheter position.

The fourth accessory port (white) is used for over-the-guidewire (OTW) introduction and positioning of the catheter in the retro-hepatic inferior vena cava. This lumen also has a small port opening along the catheter shaft positioned inferior to the caudal balloon and exits at the distal tip, to allow inferior vena cava blood, proximal to the caudal balloon, to bypass the occluded segment of the inferior vena cava and flow into the right atrium.

2. Accessory Pack

- 9F and 13F Dilator Set --These over-the-wire dilators are used to widen the subcutaneous space and venous entry site in preparation for the placement of the 18F Introducer Set.
- 18F Introducer Set (Sheath and Dilator) -- The 18F introducer sheath and coaxial dilator are to be placed over a wire; the dilator is removed, and the sheath is available for the insertion of the Double Balloon Catheter or the 18F Obturator.
- 18F Obturator -- An 18F obturator is used to occlude and support the 18F sheath lumen when it is not in use, and upon removal of the Double Balloon Catheter at the end of the procedure.
- 5F Introducer Set (Sheath and Dilator) -- A 5F hemostasis sheath is used to facilitate the introduction of the 5F Infusion Catheter through the femoral artery.
- 10F Introducer Set (Venous Return Sheath) -- A 10F sheath used to return the filtered hepatic venous blood through the internal jugular vein. A 3-way high-flow stopcock is included as part of the 10F Introducer Set. The high-flow stopcock is attached to the Venous Return Sheath and then to the male connector of the Extracorporeal Hemofiltration Circuit, if required. This sheath may also be used for hydration.

3. 5F Infusion Catheter -- 5F arterial catheter is used to deliver Hepzato into the proper hepatic artery or it can be used to coaxially introduce a microcatheter, if, at the discretion of the Interventional Radiologist, a microcatheter is preferred for selective catheter tip placement for the drug infusion. The following microcatheters have been qualified for use with the Hepzato KIT™ - select one of the microcatheters below. See microcatheter manufacturer's Instructions for Use. These microcatheters are NOT PROVIDED by Delcath:

- Merit Maestro (Merit Medical Systems, Inc., So. Jordan, UT, USA)
- Boston Scientific Renegade Hi-Flo (Boston Scientific Corp., Natick, MA, USA)
- Terumo Progreat (Terumo Medical Corp., Somerset, NJ, USA)

4. Delcath Hemofiltration Dual Filter Cartridge -- One single-use Dual Filter Cartridge designed with the filter cartridges arranged in parallel to lower the concentration of Hepzato (melphalan) in systemic circulation. The cartridge frame comes with a built-in pole clamp.

Filter mechanism of action: The filter is composed of activated carbon for adsorption and removal of HEPZATO. The pore structure of the filter media along with its particle size and shape contribute to rapid HEPZATO adsorption where large quantities (70 cc/100 g of carbon with melphalan) are adsorbed during a first pass through the filter Flow rates should be between 0.4 Liters/minute to 0.8 Liters/minute, to ensure the appropriate removal of the HEPZATO from the blood during the 30-minute infusion period and continue to remove residual drug during the 30-minute wash out period.

5. Extracorporeal Hemofiltration Circuit (EFC)- The Extracorporeal Hemofiltration Circuit is used to transport the hepatic venous blood, which has been isolated by the Double Balloon Catheter and aspirated into the fenestration lumen, through the Hemofiltration Cartridges and back to the patient through the Venous Return Sheath. Connections are provided for infusion of normal saline. This circuit includes:

- Medtronic AP40 AffinityTM CP Centrifugal Pump (“Pump Head”), a disposable pump head to be used with a pump console manufactured by Medtronic, Inc. - see manufacturer's Instructions for Use for Pump Head. (Note: The Medtronic, Inc. Bio-Console 560 (extracorporeal blood pumping) System is required for use with the Hepatic Delivery System: This is NOT PROVIDED by Delcath).
- Medtronic Bio-Probe® DP-38P blood flow monitoring insert (“Flow Probe”), a disposable flow probe to be used with a blood flow monitoring transducer manufactured by Medtronic, Inc. - see manufacturer's Instructions for Use for Flow Probe. The Flow Probe is used to measure the rate of blood flow during the procedure. (Note: The Medtronic Bio-Probe TX50P blood flow monitoring transducer is required for use with the Hepatic Delivery System: This is NOT PROVIDED by Delcath).
- Prime/Flush Line to be used to prime the system and flush the filter after system is fully de-bubbled (de-gassed).
- Pressure Monitoring Lines allow measuring the positive and negative pressure pre- and post- pump head.
- High Flow Stopcocks to allow the CO2 Connection Line and the pressure monitoring lines to be attached to the assembled circuit.
- Venous Return Line to be attached post system prime and flush so that the circuit can be attached to the 10F Venous Return Sheath.

6. Carbon Dioxide (CO2) Connection Line -- The CO2 Connection Line is used to deliver sterile CO2 gas to the Hemofiltration Cartridges to aid in priming/debubbling the filter cartridge, prior to the start of the procedure. The CO2 Line has no patient contact.

WARNING
Only the components provided in the HEPZATO KIT or specified by Delcath Systems, Inc. in the “not included” box below are to be used to create the circuit. There should be no substitutions. The circuit has not been validated for use with other components.

Do not disassemble the components provided in the Hepatic Delivery System as this may damage the components.

NOT INCLUDED:

- Bubble Trap holder
- Medtronic Bio-Console 560 Speed Controller System (“Pump”)
- Medtronic 560A (“Motor Drive”)
- Medtronic Bio-Probe TX50P (“Flow Transducer”)
- CO2 Supply for Priming Dual Filter
- Drug Injector: must be able to inject at a rate of 25 mL/minute
- Drug Delivery Disposables:
- One (1) Medrad 150mL Syringe (Polypropylene (PP)-Barrel & Polyisoprene-Plunger) or equivalent
  - Two (2) Intravenous Administration Set with spike & drip chamber (Polyvinylchloride (PVC)-tubing, Acrylonitrile butadiene styrene (ABS) & Polyethylene (PE)-Drip Chamber & Polycarbonate (PC)-Luer) or equivalent
  - One (1) - 48” injector lines (PVC-Tubing & PC-Luer) or equivalent
  - Five (5) 3-way stopcocks (PC-body, High Density Polyethylene (HDPE) or Acetal-Handles) or equivalent
  - Three (3) 20 mL syringes (PP-Barrel & Polyisoprene-Plunger) or equivalent
- Microcatheters (Maximal Distal End OD = 2.8F) – for Selective Drug Infusion (at Interventional Radiologist discretion). Select one from Delcath qualified microcatheters listed below:
  - Merit Maestro (Merit Medical Systems, Inc., So. Jordan, UT, USA)
  - BSC Renegade Hi-Flo (Boston-Scientific Corp.; Natick, MA, USA)
  - Terumo Progreat (Terumo Medical Corp., Somerset, NJ, USA)

INDICATIONS FOR USE

HEPZATO KIT™, containing HEPZATO for injection, is indicated as a liverdirected treatment for adult patients with uveal melanoma with unresectable hepatic metastases affecting less than 50% of the liver and no extrahepatic disease or extrahepatic disease limited to the bone, lymph nodes, subcutaneous tissues, or lung that is amenable to resection or radiation.

WARNING: PERI-PROCEDURAL COMPLICATIONS, MYELOSUPPRESSION
Severe peri-procedural complications including hemorrhage, hepatocellular injury, and thromboembolic events may occur via hepatic intra-arterial administration of HEPZATO. Assess patients for these adverse reactions during and for at least 72 hours following administration of HEPZATO.
HEPZATO KIT is available only through a restricted program under a Risk Evaluation and Mitigation Strategy called the HEPZATO KIT REMS.
Myelosuppression with resulting severe infection, bleeding, or symptomatic anemia may occur with HEPZATO. Monitor hematologic laboratory parameters and delay additional cycles of HEPZATO therapy until blood counts have improved.

CONTRAINDICATIONS

HEPZATO KIT is contraindicated in patients with:

- Active intracranial metastases or brain lesions with a propensity to bleed
- Liver failure, portal hypertension, or known varices at risk for bleeding
- Surgery or medical treatment of the liver in the previous 4 weeks
- Uncorrectable coagulopathy
- Inability to safety undergo general anesthesia, including active cardiac conditions including, but not limited to, unstable coronary syndromes (unstable or severe angina or myocardial infarction), worsening or newonset congestive heart failure, significant arrhythmias, or severe valvular disease
- History of allergies or known hypersensitivity to melphalan
- History of allergies or known hypersensitivity to a component or material utilized within the HEPZATO KIT including:
  - History of allergy to natural rubber latex
  - History of allergy or hypersensitivity to heparin or presence of heparin-induced thrombocytopenia (HIT)
  - History of severe allergic reaction to iodinated contrast not controlled by premedication with antihistamines and steroids

WARNINGS AND PRECAUTIONS

PLEASE CAREFULLY READ AND UNDERSTAND THE LIST OF WARNINGS AND PRECAUTIONS BELOW AS SERIOUS INJURY, ILLNESS OR DEATH OF THE PATIENT CAN OCCUR IF THESE WARNINGS AND PRECAUTIONS ARE NOT PROPERLY FOLLOWED.

Peri-Procedural Complications

Hemorrhage, hepatocellular injury, and thromboembolic events have been observed when HEPZATO has been administered via hepatic intra-arterial administration. Administration of HEPZATO KIT requires general anesthesia and extracorporeal bypass of circulation which may cause life threatening or fatal adverse effects. Ensure the patient is euvolemic but do not overhydrate the patient. Monitor for these peri-procedural complications during the procedure and for at least 72 hours following the procedure.

To mitigate the risk of thromboembolic events, administer anticoagulation as described in the IFU during the procedure.

Due to the risk of bleeding, do not use in patients with uncorrectable coagulopathies and delay treatment with the HEPZATO KIT for at least 4 weeks after surgery or other medical procedure involving the liver. Platelets and clotting factors may be removed during the HEPZATO KIT procedure. Monitor platelets and coagulation parameters as described in the IFU. If lifethreatening bleeding occurs during the procedure, reverse anticoagulation as described in the IFU and correct coagulopathy as appropriate. Discontinue anticoagulation with warfarin or other oral anticoagulants prior to the procedure until hemostasis has been restored after the procedure and no bleeding complications have been observed. Refer to the Prescribing Information of the anticoagulant agent for bridging recommendations for anticoagulation prior to surgical procedures. Discontinue drugs affecting platelet function such as aspirin, non-steroidal anti-inflammatory drugs, or other antiplatelet drugs one week before the procedure.

Patients with abnormal hepatic vascular (especially arterial supply) or biliary (especially re-implantation of bile duct) anatomy or gastric acid hypersecretion syndromes may be at increased risk of peri-procedural complications or other severe adverse reactions. Screen patients for a history of prior surgeries involving the bile duct to assess whether the patient is an appropriate candidate for HEPZATO KIT and monitor patients for adverse reactions following HEPZATO KIT administration.

Procedure-related reductions in blood pressure including severe hypotension can occur during the HEPZATO KIT procedure. Closely monitor blood pressure during the procedure. Patients may require fluid support and vasopressors. To reduce the risk of severe hypotension, assess hypothalamic-pituitary-adrenal axis function, and temporarily discontinue ACE-inhibitors, calcium channel blockers, or alpha-1-adrenergic blockers for at least 5 half-lives prior to treatment with the HEPZATO-KIT. If necessary, use other short-acting antihypertensive drugs to manage blood pressure during the peri-procedure period.

HEPZATO KIT REMS Program

The HEPZATO KIT is only available through a restricted program under a REMS, because of the risk of severe peri-procedural complications including hemorrhage, hepatocellular injury, and thromboembolic events defined in the REMS. The HEPZATO KIT should only be used by trained healthcare providers [see HEPZATO USPI Warnings and Precautions (5.2)].

Important requirements of the HEPZATO KIT REMS include:

Healthcare settings that dispense and administer HEPZATO KIT must be enrolled, certified, and comply with the REMS requirements.

Certified healthcare facilities must ensure that healthcare providers who perform the Percutaneous Hepatic Perfusion (PHP) procedure are trained on the use of HEPZATO KIT and must only dispense HEPZATO when authorized to do so.

Certified healthcare facilities must ensure that patients are assessed for severe peri-procedural complications during the procedure and for at least 72 hours following the procedure.

Further information is available at www.HEPZATOKITREMS.com or contact Delcath Systems at 1-833-632-0457.

Myelosuppression

Hematologic adverse reactions, including thrombocytopenia, anemia, and neutropenia have been reported in patients treated with HEPZATO. The risk of hematologic adverse reactions may be increased in patients who have received prior chemotherapy, bone irradiation, or who have compromised bone marrow function.

In the 95 patients who received HEPZATO KIT in the FOCUS trial, 68% had Grade 3 or 4 myelosuppression. A total of 55%, 33%, and 30% experienced Grade 3 or 4 thrombocytopenia, anemia, and neutropenia, respectively. Median time to thrombocyte nadir was 13 days (range: 3-33) after treatment with median recovery in 20 days (range: 4-29) after treatment. Median time to hemoglobin nadir was 10 days (range: 3-21) after treatment with median recovery in 13 days (range: 4-28) after treatment. Median time to neutrophil nadir was 11 days (range: 3-36) after treatment with median recovery in 17 days (range: 9-36) after treatment.

Monitor patients for severe infections, bleeding, and symptomatic anemia. Only administer HEPZATO in patients with platelets >100,000/microliter, hemoglobin ≥10.0 gm/dL and neutrophils >2,000/microliter. Administer transfusions or growth factors as appropriate [see HEPZATO USPI Dosage and Administration (2.1)].

Hypersensitivity Reactions

Hypersensitivity reactions, including anaphylaxis, have occurred in approximately 2% of patients who received an intravenous (IV) formulation of melphalan. These reactions with melphalan are characterized by urticaria, pruritus, edema, skin rashes, and in some patients, tachycardia, bronchospasm, dyspnea, and hypotension. Hypersensitivity can occur in patients with or without prior exposure to IV or oral melphalan.

When a hypersensitivity reaction is observed, immediately terminate the hepatic arterial melphalan infusion and administer necessary supportive care [see HEPZATO USPI Contraindications (4), and Adverse Reactions (6.1)].

Patients with a history of allergic reactions to iodinated contrast may experience hypersensitivity reactions, including anaphylaxis, during treatment with the HEPZATO KIT. Premedicate patients with a history of allergic reaction to iodinated contrast prior to treatment with HEPZATO KIT. Do not administer HEPZATO KIT in patients with a history of severe allergic reactions or anaphylaxis to iodinated contrast [see IFU contraindications and HEPZATO USPI Contraindications (4)].

Gastrointestinal Adverse Reactions

Gastrointestinal adverse reactions including nausea and vomiting, abdominal pain, and diarrhea are common, and occurred in 84% of patients treated with HEPZATO KIT in the FOCUS trial. Administer a proton-pump inhibitor (PPI) the day prior to and the morning of the procedure. If anti-emetic treatment is required, pre-medicate with anti-emetic therapy in subsequent cycles.

Secondary Malignancies

Melphalan has been shown to cause chromatid or chromosome damage in humans. Secondary malignancies, including acute nonlymphocytic leukemia, myeloproliferative syndrome, and carcinoma, have been reported in patients with cancer treated with intravenous alkylating drugs including melphalan. Some patients also received other chemotherapeutic agents or radiation therapy. Precise quantification of the risk of acute leukemia, myeloproliferative syndrome, or carcinoma is not possible. Published reports of leukemia in patients who have received oral or IV melphalan (and other alkylating drugs) suggest that the risk of leukemogenesis increases with chronicity of treatment and with cumulative dose [see HEPZATO USPI Nonclinical Toxicology (12.1)].

Embryo-Fetal Toxicity

Based on animal studies and its mechanism of action, melphalan can cause fetal harm when administered to a pregnant woman. Melphalan is genotoxic, targets actively dividing cells, and was embryolethal and teratogenic in rats. Advise pregnant women of the potential risk to a fetus. Advise females of reproductive potential to use effective contraception during treatment with melphalan and for 6 months after the last dose. Advise males with female partners of reproductive potential to use effective contraception during treatment with HEPZATO and for 3 months after the last dose [see HEPZATO USPI Use in Specific Populations (8.1, 8.3), Nonclinical Toxicology (13.1)].

Infertility

Melphalan-based chemotherapy regimens have been reported to cause suppression of ovarian function in premenopausal women, resulting in persistent amenorrhea in approximately 9% of patients. Reversible or irreversible testicular suppression has also been reported [see HEPZATO USPI Use in Specific Populations (8.3)].

LOCATION OF PROCEDURE

The procedure must be performed in an appropriately equipped interventional radiology suite with fluoroscopy or an operating room designed and equipped similarly. Resuscitation personnel, equipment, and medications must be immediately available.

Percutaneous Hepatic Perfusion (PHP)
PROCEDURE TEAM
PHP Procedure team members are the Interventional Radiologist, the Perfusionist and the Anesthesiologist.

A qualified interventional radiologist with the knowledge, skills, experience, and hospital privileges required to perform advanced vascular interventional procedures.

A qualified perfusionist to establish, monitor, and control the extracorporeal pump and veno-venous bypass circuit.

A qualified anesthetist (anesthesiologist) and/or nurse anesthetist responsible for the management of sedation, analgesia, respiratory and cardiovascular support.

The PHP procedure team (IR, PF, AN) is required to complete the Risk Evaluation and Mitigation Strategy (REMS) training. Refer to Procedure Flowchart (Figure 35) which provides an overview of the procedure and how the PHP procedure team and their tasks work together. All REMS materials are available at www.HEPZATOKITREMS.com or by calling the REMS Coordinating Center at 1-833-632-0457.

To facilitate use of these instructions, the procedural sections include Healthcare User Identifiers to assist each user in identifying procedural steps applicable to them.

OTHER CLINICAL TEAM MEMBERS

Other clinical team members include the medical/surgical oncologist, pharmacist, chemotherapy healthcare professional and intensivist.

A qualified medical/surgical oncologist experienced in the monitoring of toxicities of chemotherapy and who is responsible for the complete medical management of the patient, including, but not limited to, pre- and post-operative care. The medical/surgical oncologist may also be responsible for monitoring the patient during the immediate post-procedure period.

•

The medical/surgical oncologist will also play a unique role in communicating about chemotherapeutic agent (HEPZATO) and the Hepatic Delivery System risks and coordinating with other oncologists and key health care professionals responsible for patient follow-up care and monitoring for post-procedure toxicities.

A qualified pharmacist, on call during the procedure, to reconstitute the chemotherapeutic agent HEPZATO (melphalan), using national and local safety guidelines. The pharmacist should be aware of the rapid preparation time required for the preparation and administration of HEPZATO for use with the Hepatic Delivery System.

A qualified chemotherapy healthcare professional certified by the site to deliver chemotherapy, such as Interventional Radiology Technician or Registered Nurse.

A qualified intensivist, or appropriately qualified critical care specialist, responsible for providing medical management (reversing coagulopathy and blood product support) of the patient in the immediate post-procedure period during which the patient is in the intensive care unit or step-down unit.

PROCEDURE

PREPARATION: PRIOR TO TREATMENT

All medications and supportive measures must be determined and administered in accordance with each institution's policies, guidelines, procedures, and the HEPZATO KIT prescribing information.

Before starting the procedure, confirm that all components of the HEPZATO KIT are available for assembly. Note: Certain components are not supplied by Delcath. Verify that the Medtronic pump is functioning properly (see pump operating manual for instructions on proper functionality).

Hepatic Vascular Mapping - Angiography and Embolization

To deliver HEPZATO to the whole liver and avoid inadvertent infusion of HEPZATO into the gastrointestinal or visceral branches, conduct a thorough hepatic artery angiogram and investigation of variant hepatic and gastric artery anatomy. In addition, embolization of certain branches supplying the gastro-intestinal tract may be necessary.

WARNING

If the perfusion of melphalan cannot be isolated from the systemic circulation, stop the drug infusion immediately.

- Evaluate the portal vein for patency with late imaging during celiac and superior mesenteric arteriography. The presence of portal venous hypertension is a contraindication for treatment with HEPZATO via the HEPZATO KIT.
- Completely examine the arterial supply to the liver and assess and understand its impact on chemotherapy infusion. Use of a selective micro-catheter may facilitate both embolization and subsequent drug infusion.
- Assess liver blood supply and formulate a strategy for catheter placement to ensure drug infusion to the entire liver. If the risk assessment is unfavorable or the anatomic variation is too complex to allow whole liver or sequential lobar catheterization for safe delivery of melphalan, the procedure must not be performed.
- Depending on vascular anatomy, a sequential lobar approach may be the best administration option which requires splitting the HEPZATO dose. This will require repositioning of the catheter during the procedure.
- A whole liver infusion (dosing) approach will likely require embolization of the gastroduodenal artery but depends on its origin relative to the side branches of the distal proper hepatic artery. If the infusion catheter tip can be placed sufficiently distally to avoid retrograde reflux into the gastroduodenal artery, then the latter may not need to be embolized.

Double Catheter Balloon Sizing

- The double catheter balloon has two sizes representing the inter-balloon spacing distance. Spacing is based on hepatic venous anatomy and avoidance of renal vein occlusion. An inter balloon sizing should assure full isolation of all hepatic veins without occluding renal veins. Review computed tomography or magnetic resonance imaging to assess venous anatomy. Select KIT (balloon spacing) based on patient anatomy.

Coagulation Studies

- Perform coagulation studies pre-, peri- and post-procedure then repeat until normalized. Parameters tested must include:
  - Partial Thromboplastin Time
  - Prothrombin Time / International Normalized Ratio

Blood Products

Type and cross-match depending on institutional guidelines for:

- Red blood cells
- Fresh Frozen Plasma
- Platelets
- Cryoprecipitate

Hydration

- Pre procedural hydration is required if patient is determined to be hypovolemic. Do not over hydrate the patient pre-, peri- or post procedure. Overhydration has been associated with procedural and post-procedural complications.
- Procedural hydration is required since 700 mL or more of blood will be displaced into the extracorporeal circulation. A mixture of colloids and crystalloids are used to replace this volume and steadily maintain mean arterial pressure above 60 mmHg during the procedure. Typically, total procedural fluid requirements range between 1,500 and 3,000 mL.
- A Foley catheter is recommended to closely monitor fluid balance during hydration. If the patient is stable, remove within 24 hours after the procedure.

Allopurinol

- As a prophylaxis for electrolyte abnormalities, patients with more than 25% replacement of normal liver parenchyma with tumor are to be given allopurinol 300 mg/day orally beginning two (2) to three (3) days prior to percutaneous hepatic perfusion (PHP) with the Hepatic Delivery System and continuing two (2) to three (3) days following procedure.

Proton Pump Inhibitors

- Administer prophylactic proton pump inhibitors (for example: omeprazole, one 20 mg delayed release capsule by mouth) the day before and the morning of the procedure.

Anticoagulation

- The patient will be systemically anticoagulated with heparin during the procedure. Systemic anticoagulation is required to reduce the risk of thrombus formation including formation of thrombi that may impede free extracorporeal flow and filtration. Activated clotting time must be closely monitored to ensure adequate anticoagulation.
  - Obtain the baseline activated clotting time value.
  - Administer heparin to the patient only AFTER placement of the 18F (femoral vein), 10F (jugular vein), and 5F (femoral artery) sheaths. Ultrasound guidance and single anterior wall puncture technique are recommended during sheath placement to avoid bleeding complications.
  - The patient must be fully heparinized prior to the insertion of the Double Balloon Catheter into the inferior vena cava. Begin with an initial intravenous bolus of heparin at 300 units/kg, dose adjusted to achieve activated clotting time.
  - A minimum activated clotting time (ACT) of 400 seconds is necessary with a recommended ACT value > 450 seconds
  - Evaluate activated clotting time frequently (approximately every 5 minutes) until adequate anti-coagulation is established (ACT > 400 seconds).
  - DO NOT insert double balloon catheter into the patient Until ACT values are > 400 seconds.
  - Maintain activated clotting time at > 400 seconds throughout the procedure, assessing ACT values every 15 – 30 minutes depending on the patient's response and administering intravenous heparin as needed.

Anesthetic Management

- Treatment must be administered with patients being monitored and under general anesthesia. Emergency resuscitation equipment must be available during the procedure.

Blood Pressure Control

- Expect significant procedure related decrease of blood pressure when the balloons occlude blood return from the inferior vena cava (decreased cardiac inflow) and when the filters are brought into the extracorporeal bypass circuit. The reasons for filter-related hypotension are multifactorial, but hypersensitivity to non-physiological surfaces (inflammatory response), significant reduction in venous return and preload, and possible removal of catecholamines by the filters may play a role. To aid blood pressure maintenance for extracorporeal bypass, the following actions are recommended per institutional practice:
  - Pre-operative hydration and intra-procedural administration of colloids and crystalloids.
  - Vasopressor use in accordance with institutional practices to elevate mean arterial pressure to a target >65 mmHg
- Blood pressure must be constantly monitored throughout the procedure and maintained at levels required for adequate perfusion of critical endorgans (i.e., >65 mmHg).

Drug Preparation and Delivery Planning

- Prior to set up, provide pre-notification to the hospital pharmacy to be ready to reconstitute HEPZATO for injection.
- HEPZATO reconstitution and delivery should be coordinated and timed so that the start of the infusion of the melphalan is within thirty minutes of preparation. Drug administration should be completed within 60 minutes of the start of preparation.
- The filters should not be brought online until HEPZATO is in the procedure room. This minimizes filtration duration and associated complications.

PREPARING AND PRIMING THE EXTRACORPOREAL HEMOFILTRATION CIRCUIT (EFC)

CAUTION: Adherence to strict sterile procedures is always mandatory

1. Assemble EFC

See Figure 1 (Assembled System) for reference to a completely assembled circuit.

(a) Utilizing strict aseptic technique, heparinize nine (9) liters of 0.9% Sodium Chloride Injection (normal saline) by adding 2,000-5,000 units of heparin per liter.
(b) Remove Hemofiltration Dual Filter Cartridge from sterile pouch.
(c) Attach the filter to the intravenous pole using the built-in pole mount clamp, see Figure 3.
  Figure 3: Filter mount
(d) Refer to “THIS END UP” label on filter faceplate, see Figure 4.
  Figure 4: Filter Orientation
(e) Open the circuit tray and remove the components that are in the pouches. Set aside for later assembly.
(f) Remove the “Filter Inflow Assembly” and “Pump Head Assembly” sections from the circuit tray, see Figure 5.
  1. Connect Filter Inflow Assembly to Pump Head outlet
  2. Connect DBC Assembly to Pump Head inlet
  3. Place pump head on the pump drive motor
  4. Insert flow probe into flow transducer
  Figure 5: Filter Inflow Assembly
(g) Connect the two Inflow lines (labeled and identified as in Figure 6) to the cartridge inlet connectors located on the bottom of the dual filter. To complete the assembly, push each of the quick connector couplings together, as shown in Figure 6 (male to female) until an audible “click” is heard to verify connection (push and click).
  Figure 6: Filter Inflow Assembly Connection
(h) Remove the “Filter Outflow Assembly” section from its sterile pouch, see Figure 7.
  Figure 7: Filter Outflow Assembly Connection
(i) Connect the two outflow lines to the filter cartridge outlet connectors located on the top of the dual filter using the quick connector couplings (push and click). Identify assembly labels as in Figure 8.
  Figure 8: Filter Outflow Line Connection
(j) Assemble the two ends of the bypass line by pushing the quick connectors together (push and click), see Figure 9 (black circle).
  Figure 9: Bypass Line Assembly
(k) Remove the “Prime/Flush Line” from its sterile pouch
  1. Attach the female quick connect on the prime/flush line to the male quick connect coupling of the filter outflow assembly located distal to “Y”connector at F (Blue Arrow), as shown in Figure 10
  2. Place the open end of the “Prime/Flush Line” into the basin for collecting the flushed effluent during filter hydration
  Figure 10: Prime Flush Line Assembly Connection
(l) Attach the supplied stopcocks as outlined in Figure 11 identified by the blue circles to the:
  1. “B” (pre-pump head pressure/suction)
  2. “D” (pre-filter pressure)
  3. “F” (outlet) Y-connector ports
  4. Check that all stopcocks are in the closed position (lever closed to the perfusion circuit)
  5. Verify “Bypass Line” clamp 4 is open (Blue Arrow)
  Figure 11: Stopcock Attachment Locations
(m) System CO2 Prime (see Figure 12):
  1. Close outlet clamp (11). Note that clamps 1-10 are open
  2. Attach the CO2 connection line to the stopcock “F” and open the stopcock
  3. Connect the open end of the CO2 connection line to the CO2 source
  4. Set the CO2 source regulator to 3psi (approximately 3 liters per minute (LPM))
  5. Start the CO2 gas flow and allow the CO2 to flow through the extracorporeal hemofiltration circuit. Note that CO2 flow is retrograde through the tubing set exiting at IV spikes (clamps 1 &2) and blue sterile pouch (clamp 3)
  6. Adjust CO2 regulator to maintain 3psi (as necessary). Verify CO2 flow through the circuit
  7. Close bypass clamp (4) after approximately 1 minute to ensure flow through the hemofiltration cartridges
  8. Allow CO2 to flow through the cartridges (after closing clamp 4) for at least 5 minutes but preferably 15 minutes
  9. After the desired CO2 prime duration, close the following clamps to pressurize the system with CO2 and prevent room air from entering:
    1. Saline spike clamps (1, 2)
    2. Double balloon catheter line clamp (3)
    3. Filter inlet clamps (5, 6)
    4. Filter outlet clamps (7, 8)
  10. Stop the CO2 flow and close the stopcock “F”
  11. Disconnect the CO2 connection line and discard
  Figure 12: CO2 Priming Connections
(n) Hang two bags of the heparinized sterile normal saline and connect to circuit by using the spikes, as shown in Figure 13, to allow for gravity priming of circuit components. CAUTION: Use strict aseptic technique while spiking the heparinized normal saline bags.
  Figure 13: Connecting Heparinized Saline Bags

2. Prime Double Balloon (Isolation Aspiration) Catheter Line

(a) Close pre-pump clamp (10).
(b) Confirm that stopcock “B” is in the closed position (the lever is pointed toward the circuit tubing to the right).
(c) Open double balloon catheter line clamp (3).
(d) Open saline line (clamp 1 or 2), to allow heparinized normal saline to prime line only up to clamp 3, see Figure 14; (e) blue arrows demonstrating flow direction. Do not allow excess heparinized normal saline to fill sterile wrap.
(e) Close clamp 3.
  Figure 14: Prime Double Balloon Isolation Aspiration Catheter Line

3. Prime Bypass Line and Pump Head (see Figure 15):

(a) Inspect that stopcock “D” is in the closed position (the lever is pointed toward the circuit tubing to the left).
(b) Prime the pump head and bypass lines by opening clamps 10 and 4.
(c) Close clamp 4.
  Figure 15: Priming Bypass Line

4. Prime and Flush Dual Filter Cartridge (see Figure 16 location of clamps and prime flow direction)

CAUTION: Do NOT allow heparinized normal saline bags to run dry or air will enter the system.

(a) Inspect that stopcock “F” is in the closed position (the lever is pointed upward).
(b) Open filter inlet clamps (5, 6).
(c) Open filter outlet clamps (7, 8).
(d) Open circuit outlet clamp (11).
(e) Adjust the flow of heparinized normal saline into the filter to a rate of approx. 0.5 liters per minute. Note: Hemostats (forceps) are required to adjust flow rate if using gravity.
  Figure 16: Priming Filter Cartridges
(f) Note that filter cartridges will have a mottled appearance indicating the presence of gas bubbles.
(g) Allow heparinized normal saline to flow through the filters and out the “Prime/Flush Line” for approximately 6-10 minutes or until the filter appears gas free (solid black).
(h) Once all gas appears to have been displaced, gently roll the cartridges between palm of hands to encourage trapped gas bubbles to rise. CAUTION: Do not use excessive force when rolling the plastic housing.
(i) Inspect the entire cartridge for trapped gas by turning the cartridge within housing to visualize the entire filter. If there are gas bubbles gently roll the cartridges to free the trapped gas.
(j) When Filter Cartridges are gas free, flush with an additional six (6) liters of heparinized normal saline (3 L/cartridge).
(k) Close filter clamps 5, 6, 7, 8 and outlet clamp 11.

5. Prime Venous Return Line and Bubble Trap

CAUTION: Do NOT install the Return Line with built-in Bubble Trap until flushing is complete

(a) Disconnect and dispose of the “Prime/Flush Line”, by pressing in the latch located on the female quick connect coupling and pulling it a part (refer to Figure 10).
(b) Open the Venous Return sterile pouch (see Figure 17) and remove the venous return line and built-in bubble trap.
  Figure 17: Venous Return Line with Built-In Bubble Trap
(c) Attach the female quick connect of the venous return line to the male quick connector (push and click) located (blue arrow) by outlet clamp (11), as shown in Figure 18. Position the bubble trap in the bubble trap holder higher than filter cartridges.
  Figure 18: Connecting Venous Return Line with Built-In Bubble Trap
(d) Attach stopcock to bubble trap and use syringe to aspirate air, as necessary, see Figure 19.
(e) Prime venous return line and bubble trap by opening clamps 4, 11 and 9
(f) Prime up to clamp 9. Do not allow saline to enter blue sterile pack.
(g) Close clamp 9 once venous return line and bubble trap are primed up to clamp 9.
  Figure 19: Priming Venous Return Line with Built-In Bubble Trap

6. Install Pressure Monitoring Lines

(a) Attach pre-pump (to measure negative pressure – pump suction) pressure monitoring line to stopcock “B” and prime, see Figure 20.
  Figure 20: Attach and Prime Pre-Pump Pressure Line
(b) Attach pre-filter (to measure positive pressure – pre-filter) pressure monitoring line to stopcock “D” and prime, see Figure 21.
  Figure 21: Attach and Prime Pre-Filter (Post-Pump) Pressure Line
(c) Attach the pressure monitoring lines to the P1 and P2 ports on the rear of the Medtronic Bio-Console 560 Speed Controller System.
(d) Zero the pressure transducers (refer to Medtronic Bio-Console 560 System Manual for details).

7. Pressure Test Circuit

(a) Pressure test circuit by slowly ramping up the pump head speed (RPM) until a pressure reading of 300 mmHg is achieved on the pressure transducer attached to the line on Y-connector “D” (pre-filter).
(b) Visually inspect all connections and cartridges to ensure no leaks are present.
  CAUTION: If leak is noted, ensure connections are secure before proceeding.
(c) Turn off pump and close cartridge inlet (5, 6) and outlet (7, 8) clamps. Ensure bypass line clamp (4) is open.
(d) System is now primed, hydrated, de-bubbled, and ready for use.
(e) Ensure there are two (2) liters of normal saline available for later use.

WARNING

Ensure that all air is purged from the system prior to use in order to avoid an air embolism

PLACING THE CATHETERS

8. Insertion of the 10F Venous Return Sheath

(a) Attach the stopcock to the sheath side port tube.
(b) Using standard Seldinger technique (recommended ultrasound guidance), insert the venous return sheath, into the internal jugular vein (preferably the right side internal jugular vein, see Figure 22). Use of sonographic guidance and a single anterior wall puncture of the vein is recommended to avoid inadvertent carotid artery puncture. If carotid artery puncture occurs, the procedure must be aborted and postponed to a later date, due to hemorrhage risk with high level of anticoagulation.
(c) Flush the sheath with sterile heparinized normal saline.
(d) Close the stopcock.
  Figure 22: Placing Venous Return Sheath into Internal Jugular Vein

9. Insertion of the 5F Femoral Arterial Sheath

(a) Using Seldinger puncture technique and standard fluoroscopic and arteriographic techniques, place the 5F Introducer Sheath into the femoral artery, see Figure 23.
(b) Recommend sonographic guidance and a single anterior wall puncture of the femoral artery over the femoral head to assure compressibility of the artery when the sheath is removed. If a supra-inguinal puncture is made, the procedure must be aborted and postponed to a later date.
  Figure 23: Placing Femoral Artery Sheath

10. Insertion of the 18F Venous Sheath

(a) Using Seldinger technique and standard fluoroscopic and angiographic techniques, place the 18F introducer sheath into the femoral vein after serial dilation with 9F and 13F dilators. The venous sheath may be placed ipsilateral or contralateral to the 5F femoral arterial sheath placement, see Figure 24.
(b) Flush the sheath with sterile heparinized normal saline.
(c) Recommend use of sonographic guidance and a single anterior wall puncture of the femoral vein over the femoral head to assure compressibility of the vein when the sheath is removed. If a supra-inguinal puncture is inadvertently made, the procedure must be aborted and postponed to a later date.
  Figure 24: Placing Femoral Venous Sheath

11. Insertion of 5F Infusion Catheter

(a) Introduce the 5F Infusion catheter through the sheath and manipulate it over a guidewire into the proper hepatic artery, see Figure 25. At the discretion of the Interventional Radiologist, a microcatheter may be coaxially introduced through the 5F catheter for selective catheter tip placement for drug infusion. If a microcatheter is used, attach a rotating hemostatic valve (Touhy-Borst type) to the 5F catheter and insert the microcatheter into the 5F catheter through the valve. Three microcatheters have been qualified by Delcath for use with the HEPZATO for Injection/Hepatic Delivery System. Select one of the three microcatheters qualified (see Description of System Components (pg. 5).

WARNING

To deliver melphalan to the whole liver and avoid inadvertent infusion of melphalan into the gastrointestinal or visceral branches, conduct a thorough hepatic artery angiogram and investigation of variant hepatic and gastric artery anatomy. In addition, embolization of certain branches supplying the gastro-intestinal tract may be necessary.

The catheter must be positioned as described below so that drug Is infused ONLY into the liver. Perfusion of drug into any other abdominal organ or gastrointestinal branches must be avoided as this may result in serious injury or death.

(b) Position the infusion catheter (5F catheter or microcatheter) in the hepatic artery for intra hepatic HEPZATO administration and to exclude HEPZATO delivery into extrahepatic gastric side branches either directly or in the case of reflux. Affix the 5F catheter to the skin at the groin.
(c) Connect the infusion catheter (5F catheter or microcatheter) to the drug delivery system (see step 18) and maintain catheter patency by hospital catheter infusion protocols (e.g., infuse heparinized normal saline: The concentration of heparin should be 1,000 units per 500 mL of normal saline).
  Figure 25: Insertion of Hepatic Artery Infusion Catheter

ESTABLISHING ANTICOAGULATION & PLACING DOUBLE BALLOON CATHETER

12. Anticoagulation

(a) DO NOT place the double balloon catheter until the patient is fully anticoagulated.
(b) DO NOT administer heparin until the placements of all vascular sheaths.
(c) Obtain the baseline activated clotting time value.
(d) Administer heparin.
(e) Administer an initial intravenous bolus of 300 units/kg of heparin. Heparin dose should be adjusted to achieve a minimum activated clotting time of 400 seconds prior to initiation of veno-venous bypass and balloon inflation.
(f) Evaluate activated clotting time frequently (approximately every 5 minutes) until adequate anti-coagulation is established (activated clotting time > 400 seconds). Maintain activated clotting time at > 400 seconds (preferably > 450 seconds) throughout the procedure, obtaining ACT values every 15-30 minutes depending on the patient's response, and administering intravenous heparin as needed.

WARNING

The start of the intra-arterial infusion of the drug solution must be within 30 minutes of its preparation.

NOTE: TIMING OF CHEMOTHERAPEUTIC AGENT DELIVERY

Time the request for delivery of the chemotherapeutic agent (HEPZATO) so that the start of the intra-arterial infusion of the drug solution is within thirty minutes of its preparation. Since preparation and delivery times vary, depending upon local practices, the timing of the request is critical and should be prearranged with the pharmacist. Ideally, the time to request chemotherapeutic agent from the pharmacy would be when the patient is heparinized just prior to placing the Double Balloon Catheter.

13. Insertion of the Double Balloon Catheter

(a) Flush the Double Balloon catheter with heparinized normal saline.
(b) Introduce the Double Balloon catheter through the 18F sheath. Under fluoroscopic guidance advance it over a guidewire into the inferior vena cava and position the catheter tip at the level of diaphragmatic hiatus. Do NOT expand the balloons.
(c) Upon successful placement, remove guidewire and create a heparin lock within the “OTW” lumen to maintain patency.

CONNECTING CATHETERS TO EXTRACORPOREAL HEMOFILTRATION CIRCUIT

14. Connection of Catheter to Extracorporeal Hemofiltration Circuit

(a) Remove sterile wrap from extracorporeal hemofiltration circuit double balloon catheter line while maintaining sterility and transfer sterile end to interventional radiologist.
(b) Open saline line (clamp 1 or 2) clamp and clamp 3 to allow for a “wet connection” of the extracorporeal hemofiltration circuit to the double balloon catheter large drainage lumen with a quick connect fitting, see Figure 26. After connection is made, close saline line clamp (clamp 1 or 2, same ones opened previously). Ensure that all air is removed from the double balloon catheter.
  Figure 26: Connecting Double Balloon Catheter to Circuit
(c) Remove the sterile wrap from the extracorporeal hemofiltration circuit venous return line while maintaining sterility and transfer sterile end to the interventional radiologist and flush normal saline to fill the line.
(d) Connect the extracorporeal hemofiltration circuit venous return line to the stopcock of the 10F venous return sheath placed in the jugular vein (Venous Return Sheath tubing has a red clamp), flush normal saline through the line. When all air is removed, and line is completely filled with normal saline turn stopcock to close the side port. Ensure the stopcock (at the venous return line to sheath connection) is fully open to minimize back pressure and maximize flow through the stopcock. (“OFF” handle of stopcock turned 90° to flow path.)

15. Establishing Hemofiltration Circulation

(a) Confirm filter inlet and outlet clamps are CLOSED (5, 6, 7 and 8) (red circles), per Figure 27.
(b) Open clamp 9 (blue circles).
(c) Confirm that clamps 3, 4, 10 and 11 are open (blue circles)
(d) Start pump and slowly increase RPM control to achieve a maximum allowable flow rate which does not cause flow induced vibration or exceed the 0.80 L/min flow rate or −250 mmHg pre-pump pressure.
  - Flow rates of approximately 0.40 to 0.60 liters/minute are typical: 0.40 L/min is the minimum allowable and 0.80 L/min is the maximum allowable flow rate for this system.
  - In-line pressure transducers should be used to monitor pressures:
    - Pre pump pressure (suction side) should not be more negative than −250 mmHg, as lower pressures indicate possible catheter collapse or kink.
    - Pre-cartridge pressures (pre-filter) should not exceed 200 mmHg, as higher pressures indicate increasing filter resistance potentially due to thrombus or a kinked return line. Check filters to assure free flow and return line for kinks.
(e) The extracorporeal hemofiltration circuit is now established. Venous blood is aspirated from the central lumen through the fenestrations in the Double Balloon catheter. This blood flows through the Double Balloon catheter to the pump, through the bypass line, and returns to the patient through the venous return sheath.

CAUTION: Continuously monitor any perfusion related events including:

- Blood flowrate as displayed by the Medtronic Bio-Console
- Systolic, diastolic and mean arterial blood pressure
- Heart rate and vital signs
- Activated clotting times
- Bubble-trap for entrapped air
- Leaks from any part of the circuit

Figure 27: Establishing Hemofiltration Circulation

ISOLATING THE INFERIOR VENA CAVA

16. Expansion of Balloons

WARNING

There is an anticipated significant decrease of blood pressure following the initial occlusion of the inferior vena cava by the balloons. It is critical to maintain mean blood pressure above 65 mmHg

Vasoactive Agents Response Testing: Prior to expansion of either balloon (occlusion of inferior vena cava), administer vasoactive agent to assess patient responsiveness to this agent. It is recommended to use an infusion pump to quantify vasopressor doses during each procedural period. After balloons expansion, assess patient blood pressure for two (2) to five (5) minutes before proceeding. Significant decreases in blood pressure will occur within two (2) to five (5) minutes.

Continue to administer vasoactive agents to maintain mean blood pressures above 65 mmHg. Vasopressor agents are typically not required after the conclusion of the procedure.

(a) Perfusionist must carefully monitor the flow rate during the balloon expansion.

WARNING

Do NOT Over Expand the Balloons. Over Expansion of the Balloons Could Cause the Balloons to Burst which could result in Life-Threatening Injury.

(b) Maximum balloon expansion volumes:
  - Cephalad Balloon: 38 mL of dilute contrast medium
  - Caudal Balloon: 38 mL of dilute contrast medium
(c) Under fluoroscopy, partially expand the cephalad balloon with approximately 15 - 25 mL of dilute contrast media (e.g., 35% dilution) within the right atrium (the balloon will have a rounded appearance).
(d) With the caudal balloon collapsed, slowly retract the Double Balloon catheter until the cephalad balloon is at the junction of the right atrium and inferior vena cava. If needed, further expand the cephalad balloon until indentation of the diaphragmatic hiatus is visible at the inferior margin (the balloon will acquire an acorn shaped appearance, see Figure 28). Do not expand balloons beyond required volume to achieve an adequate seal. Never advance or retract the Double Balloon catheter when both balloons are expanded. If resistance is met during manipulation, determine the cause of the resistance before proceeding.
  Figure 28: Expansion and Placement of Cephalad Balloon
(e) Under fluoroscopy, expand the caudal balloon with dilute contrast medium until the lateral edges of the expanded balloon start to become effaced by the inferior vena cava wall.

WARNING

Never stop blood flow through the extracorporeal hemofiltration circuit for more than 30 seconds.

(f) With balloons expanded, perform a limited (retro-hepatic) inferior vena cavagram (using digital subtraction angiography technique) through the fenestrations. Prior to injection of contrast medium, reduce the pump speed to 1,000 RPM and clamp off the circuit. Inject iodinated contrast medium through the CONTRAST port to confirm that the catheter properly isolates hepatic venous flow between the balloons. The cephalad balloon must occlude the inferior vena cava just above the highest (closest to right atrium) hepatic vein, and the caudal balloon must occlude the inferior vena cava just below the lowest hepatic vein (above the renal veins) as shown in the radiographic image in Figure 29.
(g) Re-establish flow through the extracorporeal hemofiltration circuit by unclamping the circuit and returning pump RPM to deliver previous flow rate.
  Figure 29: Confirming Hepatic Venous Isolation

WARNING

Never Adjust the Position of the Double Balloon Catheter Unless Both Balloons are Fully Collapsed

(h) If the Double Balloon catheter is not in the proper position, collapse both balloons (caudal balloon first) and then reposition the catheter, while maintaining flow in the extracorporeal hemofiltration circuit.
(i) Once satisfactory position is attained (i.e., the isolated segment is well sealed), gently hold the proximal end of the Double Balloon catheter to prevent upward migration of the catheter into the right atrium. The catheter must be held due to forces that will push the balloon upwards towards the right atrium, and its position checked for the duration of the procedure (approximately 60 minutes).

CAUTION: Check Double Balloon catheter balloon positions fluoroscopically every four (4) to five (5) minutes during drug administration and filtration to ensure continued hepatic venous isolation.

BRINGING HEMOFILTRATION CARTRIDGES ONLINE

17. Bringing Hemofiltration Cartridges online

(a) HEPZATO preparation should be in the procedure room prior to bringing filters online. This reduces filter related complications and occupation of melphalan binding sites by blood components.
(b) Continuously monitor and check the patient's blood pressure as required (see “Blood Pressure Control”).
(c) Typically, each filter is brought online sequentially while leaving the bypass line open.
(d) Bring the left cartridge online by opening clamps 5 and 7 (see blue circles) allowing blood to displace the heparinized normal saline into the patient.
(e) Observe and manage blood pressure.
(f) After the heparinized normal saline in the left cartridge and its lines is fully replaced with blood, wait approximately 30 seconds and open right cartridge clamps 6 and 8 (see green circles), while keeping the bypass line open.
(g) Once the heparinized normal saline in the right cartridge and its lines is fully replaced with blood, wait approximately 30 seconds managing blood pressure.
(h) Once blood pressure is stable close the bypass line by securely closing clamp 4 (red circle), see Figure 30. Add a reusable tube clamp as a redundant bypass closure mechanism high on the bypass line in clear view of the team.
(i) Manage and stabilize blood pressure.
  Figure 30: Bringing Hemofiltration Cartridges online

WARNING

Close bypass line prior to infusion of drug. Never reopen bypass line

SETUP DRUG DELIVERY SYSTEM AND START EXTRACORPOREAL FILTRATION

18. Drug Administration and Extracorporeal Filtration

HEPZATO is prepared by Pharmacy per physician's prescription. Reconstitute each melphalan vial with 10 mL of supplied diluent.

- For doses up to 110 mg, dilute reconstituted HEPZATO in 250 mL 0.9% Sodium Chloride Injection (use one (1) 250 mL bag provided).
- For doses between 111 mg and 220 mg, divide the total dose equally into 2 and dilute each in 250 mL 0.9% Sodium Chloride Injection (total volume of 500ml using the two (2) 250 mL bags provided).

Multiple injection cycles of the diluted HEPZATO solution will be required (see delivery parameters described below).

WARNING

The start of the intra-arterial infusion of the drug solution must be within 30 minutes of its preparation in the pharmacy.

The duration of time between filters brought online and start of HEPZATO administration should be minimized on the order of < 5 minutes

- To deliver the drug solution, divide total volume into volumes within the capacity of the injector syringe.
- Deliver drug solution at a flow rate of 25mL/min. Refill syringe after each injection cycle.
- Conduct spasm check of the hepatic arteries and confirm balloon position and expansion against vena cava walls by fluoroscopy while refilling syringe.
- Continue infusion until all drug is delivered within 30 minutes. Below are the delivery parameters:
  - Total volume of 500 mL – 5 infusions of 100 mL at 25mL/min
  - Total volume of 540 mL – 5 infusions of 100 mL + infusion of 40 mL at 25mL/min
  - Total volume of 250 mL – 2 infusions of 100 mL + infusion of 50 mL at 25 mL/min
  - Total volume of 270 mL – 2 infusions of 100 mL + infusion of 70 mL at 25 mL/min

(a) Set-up drug delivery system by installing a 150 mL syringe into the drug injector and setting the injector flow rate to 25 mL/minute and enter the injection volume determined as described above. See Figure 31 for HEPZATO administration set up.
(b) Attach intravenous fluid administration sets to the other ports of the two stopcocks, as shown in Figure 31.
  Figure 31: HEPZATO Administration System Setup
(c) Prepare, label, and connect three (3) syringes: One (1) for contrast, one (1) for intra-arterial nitroglycerin (IANTG), and one (1) for normal saline. An example setup is depicted in Figure 32.
  1. Undiluted iodinated contrast agent is for checking hepatic artery spasm via CT. The contrast is injected by hand via the syringe for the arteriogram.
  2. Nitroglycerin is prepared for use, as needed, to relieve hepatic artery spasm.
  3. Normal saline is drawn into the saline syringe for priming and flushing the hepatic arterial infusion line during the procedure.
  Figure 32: Manifold Setup of for Nitroglycerin, Contrast and Saline

Draw the following volumes and concentrations of contrast, nitroglycerin, and normal saline into the three syringes of the drug delivery set-up.

Syringe | Volume and Concentration to Prepare in Syringe
Contrast | Use institutional practices for microcatheter contrast delivery
NTG | Use institutional practices
Normal Saline | 20 mL of 0.9% Sodium Chloride Injection

(d) Hang a 500 mL bag of normal saline and the chemotherapeutic agent (melphalan hydrochloride) drug solution bag on the intravenous pole and ensure the roller clamps are closed, and spike the bags, as shown in Figure 33. Visually inspect the solution for particulates. If particulates are observed, DO NOT USE.
  Figure 33: HEPZATO Administration System Setup
(e) Prime the drug delivery system with normal saline, fill injector syringe with approximately 120 mL of diluted drug. Ensure all air is purged from the system.
(f) When the extracorporeal hemofiltration circuit is running satisfactorily and the patient is hemodynamic stable, flush the hepatic arterial infusion line with normal saline to avoid directly mixing heparin with chemotherapeutic agent (melphalan hydrochloride). Connect drug infusion line to Hepatic Artery Infusion catheter (5F Catheter or microcatheter) to complete the drug delivery circuit.
(g) Perform an arteriogram to assess patency of the hepatic artery. Use undiluted iodinated contrast agent to check for hepatic artery spasm via CT. The contrast is injected by hand via the syringe for the arteriogram. In circumstances where hepatic arterial spasm is noted, administer nitroglycerin intraarterially to alleviate the spasm. Always flush the injection line with normal saline after contrast injections.

WARNING

Assess arterial patency approximately every four (4) to five (5) minutes via contrast administration during drug infusion. Administer intra-arterial nitroglycerin if arterial spasm is noted. If spasm cannot be relieved, terminate the procedure (see ending extracorporeal circulation below).

(h) Initiate administration of the 1st dose of chemotherapeutic agent (melphalan hydrochloride) through the Infusion catheter.

WARNING

Immediately stop the procedure if perfusion of drug is detected outside of the isolated region and cannot be corrected. Once the infusion of chemotherapeutic agent (melphalan hydrochloride) has started, do not collapse balloons unless administration of drug has been stopped and a full washout cycle (30 minutes) has been completed.

(i) After the prescribed dose has been fully administered, continue extracorporeal filtration for an additional 30 minutes (washout period).

ENDING EXTRACORPOREAL CIRCULATION

19. Ending Extracorporeal Circulation

(a) At the end of the 30-minute wash-out period, collapse the caudal balloon fully.
(b) Then collapse the cephalad balloon fully.
(c) Discontinue filtration by:
  1. Reducing the pump RPM to 1,000,
  2. Closing clamps 3 and 9 See Figure 34 (red circles).
  3. Stop flow by turning off the pump.
  Figure 34: Close Circuit Inflow and Circuit Return Clamps to Discontinue Extracorporeal Circulation

CATHETER REMOVAL

20. Catheter Removal

(a) When melphalan infusion is completed remove the guide catheter and infusion microcatheter from femoral artery access. The 5F arterial sheath should only be removed when coagulation status has been normalized.
(b) When washout phase is completed remove Double Balloon catheter from the femoral vein access and replace with 18F obturator. Place the obturator completely into the sheath so the obturator hub bottoms out onto the sheath hub. The 18F venous sheath should only be removed when coagulation status has been normalized.
(c) Close the stopcock or red clamp on the 10F venous return sheath side port and disconnect the venous return line from the sheath. Do not remove the 10F venous return sheath until coagulation status has been normalized.
(d) Dispose of all components appropriately in accordance with hospital, local, state, and federal biohazard guidelines.

NORMALIZATION OF COAGULATION STATUS FOR SHEATH REMOVAL

21. Normalization of Coagulation Status for Sheath Removal

(a) Administer protamine sulfate by slow intravenous infusion in a dose appropriate to the amount of heparin given and the activated clotting time.
(b) Administer 10 units of cryoprecipitate and/or Fresh Frozen Plasma based on coagulation profiles to correct remaining abnormalities, if indicated, per institutional guidelines.
(c) Repeat coagulation profile.
(d) Correct remaining coagulopathy following institutional guidelines. The following recommendations are provided for consideration:

Coagulation Profile | Action
Prothrombin time greater than 2 seconds of normal | Administer Fresh Frozen Plasma
Partial thromboplastin time greater than 5 seconds of normal | Administer protamine

(e) Measure blood platelet levels to determine if replacement is needed.
(f) Follow institutional guidelines for administration of packed red blood cells for anemia.
(g) All sheaths may be removed if the platelet count is greater than 50,000/ mm^3 and after the patient's coagulation status has normalized. Compress puncture sites until adequate hemostasis is achieved.
(h) Dispose of all components appropriately in accordance with hospital, local, state, and federal biohazard guidelines.
(i) Carefully monitor the patient until complete recovery.

PROCEDURE FLOWCHART - FIGURE 35

Manufactured by:
Delcath Systems, Inc.
Queensbury, NY 12804

Delcath is a registered trademark of Delcath Systems, Inc.
HEPZATO is a registered trademark of Delcath Systems, Inc.
HEPZATO KIT is a registered trademark of Delcath Systems, Inc.
© 2025 Delcath Systems, Inc. All rights reserved.
Medtronic's Bio-Console®, Bio-Pump, and Bio-Probe are registered trademarks of Medtronic Inc.

Recyclable Package

Principal Display Panel - Kit Label

NDC 75833-601-02

HEPZATO KIT™

(melphalan) for Injection/
Hepatic Delivery System (HDS)

REF 601002

EXP: YYYY-MM-DD

LOT: XXXXXXX

Contents:

1 - Hepatic Delivery System, 62 mm Double Balloon Catheter

1 - HEPZATO™ 5 x 50 mg/vial* (melphalan) for Injection and (2) 250 mL, 0.9% Sodium Chloride
Injection USP (secondary diluent):

WARNING: Hazardous Drug

SINGLE-DOSE VIAL

Rx Only

*HEPZATO Carton contains 5 vials of HEPZATO and 5 vials of sterile diluent:

*Each vial contains sterile, non-pyrogenic, freeze dried melphalan 50 mg, equivalent to 56 mg of
melphalan hydrochloride and 20 mg povidone.

Each vial of sterile, nonpyrogenic diluent containing 0.2 g sodium citrate, 6.0 mL propylene glycol,
0.52 mL ethanol (96%), and Water for Injection to a total of 10 mL.

Must be reconstituted with accompanying diluent and further diluted with accompanying 0.9%
Sodium Chloride Injection USP. See enclosed prescribing information for additional reconstitution
and administration instructions.

Recommended Dosage: see Prescribing Information

For intra-arterial infusion only

Store at controlled room temperature 20° to 25°C (68° – 77°F). Temperature excursions are
permitted between 15° to 30°C (59° – 86°F) [see USP Controlled Room Temperature]

Protect from light. Retain in carton.

Consult the HEPZATO KIT™ Instructions for Use prior to use.

Caution: This Double Balloon Catheter Contains Natural Rubber Latex

Which May Cause Allergic Reactions.

Delcath®

Packaged and Distributed by:

Delcath Systems, Inc.

Queensbury, NY 12804

Principal Display Panel – 50 mg Vial Label

NDC 75833-800-01

Rx Only

SINGLE-DOSE VIAL

HEPZATO ™

(melphalan) for Injection

50 mg/vial*

WARNING: Hazardous Drug

*Each vial contains sterile, non-
pyrogenic, freeze dried melphalan 50
mg, equivalent to 56 mg melphalan
hydrochloride and 20 mg povidone

For intra-arterial infusion only with
the Delcath Hepatic Delivery System

90004.B

Principal Display Panel – 10 mL Diluent Vial Label

NDC 75833-700-01

Rx Only

SINGLE-DOSE VIAL

STERILE DILUENT

for HEPZATO ™

(melphalan) for Injection

For Drug Diluent Use Only

Each vial contains 0.2 g sodium citrate, 6.0 mL
propylene glycol, 0.52 mL ethanol (96%),
and Water for Injection

Nonpyrogenic

90003.B

PACKAGE LABEL

Principal Display Panel - 0.9 g/250 mL Container Label

0.9% Sodium Chloride

Injection USP

REF L8002

NDC 0264-7800-20

DIN 01924303

HK 22617

250 mL

EXCEL® CONTAINER

Each 100 mL contains: Sodium Chloride USP 0.9 g;

Water for Injection USP qs

pH adjusted with HCl NF

pH: 5.6 (4.5–7.0); Calc. Osmolarity:310 mOsmol/liter

Electrolytes (mEq/liter): Na^+ 154; Cl^– 154

Sterile, nonpyrogenic. Single dose container. Do not use in series

connection. For intravenous use only. Use only if solution is clear

and container and seals are intact.

WARNINGS: Some additives may be incompatible. Consult with

pharmacist. When introducing additives, use aseptic techniques.

Mix thoroughly. Do not store.

Recommended Storage: Room temperature (25°C). Avoid excessive

heat. Protect from freezing. See Package Insert.

Do not remove overwrap until ready for use. After removing the overwrap,

check for minute leaks by squeezing container firmly. If leaks are found,

discard solution as sterility may be impaired.

Not made with natural rubber latex, PVC or DEHP.

Rx only

EXCEL is a registered trademark of B. Braun Medical Inc.

B. Braun Medical Inc.

Bethlehem, PA 18018-3524 USA

1-800-227-2862

www.bbraun.com

In Canada, distributed by:

B. Braun of Canada, Ltd.

Scarborough, Ontario M1H 2W4

Y94-003-223

LD-136-4

EXP

LOT